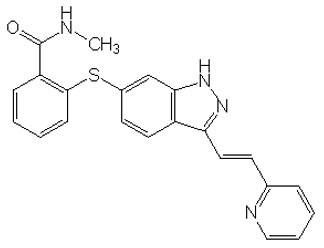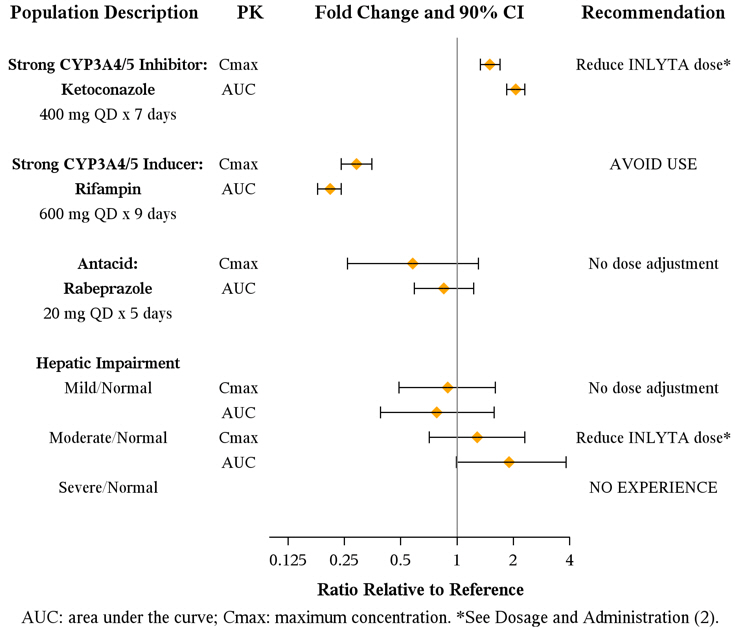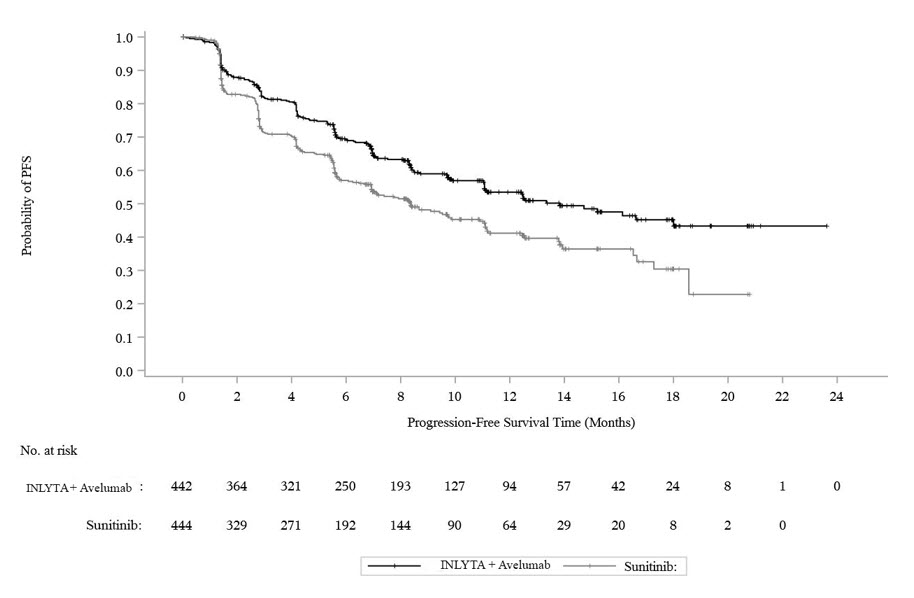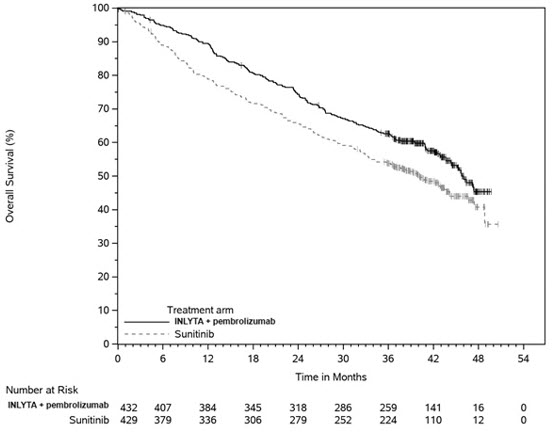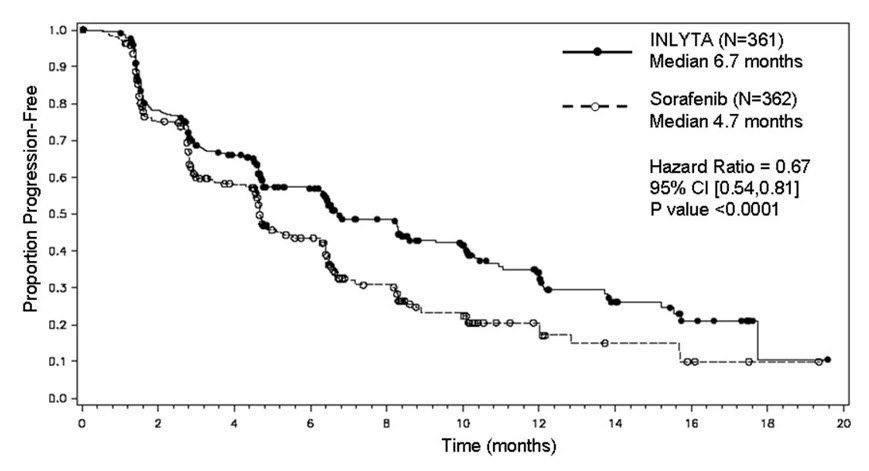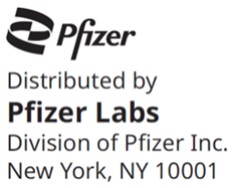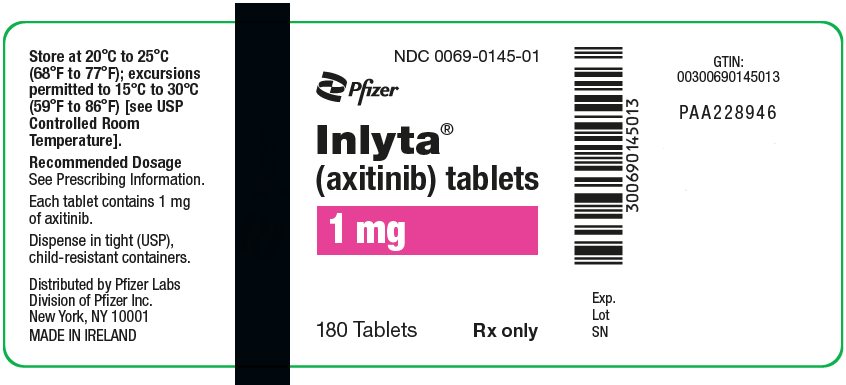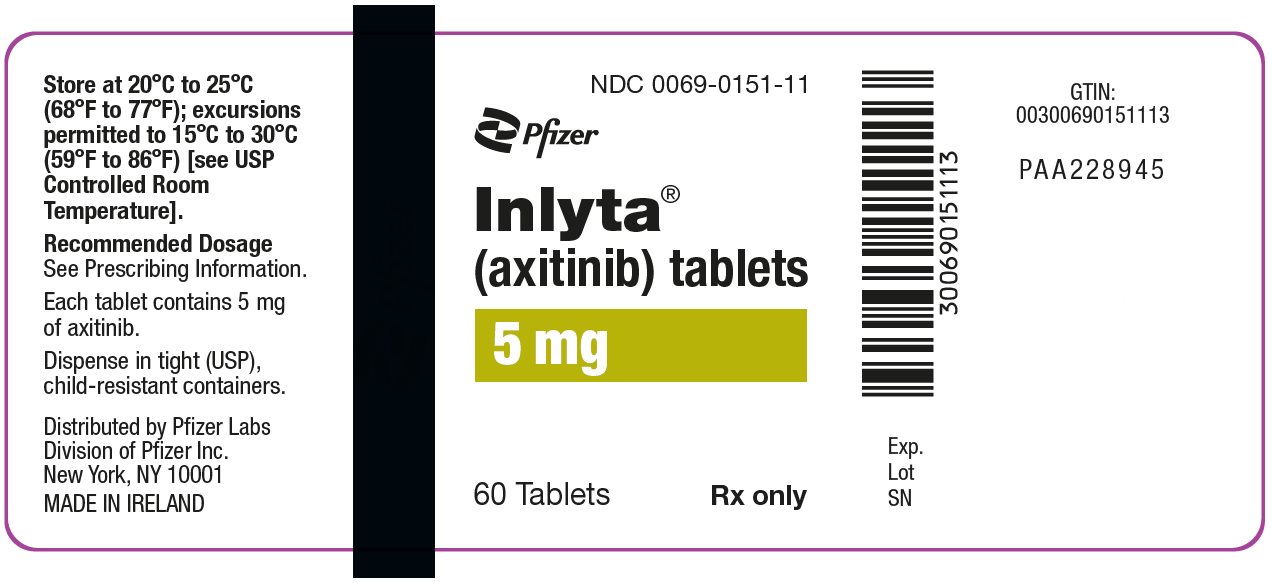 DRUG LABEL: INLYTA
NDC: 0069-0145 | Form: TABLET, FILM COATED
Manufacturer: Pfizer Laboratories Div Pfizer Inc
Category: prescription | Type: HUMAN PRESCRIPTION DRUG LABEL
Date: 20250219

ACTIVE INGREDIENTS: AXITINIB 1 mg/1 1
INACTIVE INGREDIENTS: MICROCRYSTALLINE CELLULOSE; LACTOSE MONOHYDRATE; CROSCARMELLOSE SODIUM; MAGNESIUM STEARATE; TITANIUM DIOXIDE; TRIACETIN; FERRIC OXIDE RED; HYPROMELLOSE 2910 (15000 MPA.S)

HIGHLIGHTS OF PRESCRIBING INFORMATION

These highlights do not include all the information needed to use INLYTA safely and effectively. See full prescribing information for INLYTA.
INLYTA® (axitinib) tablets, for oral administration
Initial U.S. Approval: 2012

1 INDICATIONS AND USAGE

INLYTA is a kinase inhibitor indicated:

- in combination with avelumab, for the first-line treatment of patients with advanced renal cell carcinoma (RCC). (1.1)
- in combination with pembrolizumab, for the first-line treatment of patients with advanced RCC. (1.1)
- as a single agent, for the treatment of advanced renal cell carcinoma (RCC) after failure of one prior systemic therapy. (1.2)

2 DOSAGE AND ADMINISTRATION

- INLYTA 5 mg orally twice daily with avelumab 800 mg every 2 weeks. (2.1)
- INLYTA 5 mg orally twice daily with pembrolizumab 200 mg every 3 weeks or 400 mg every 6 weeks. (2.1)
- INLYTA as a single agent the starting dose is 5 mg orally twice daily. (2.1)
- Dose adjustments can be made based on individual safety and tolerability. (2.2)
- Administer INLYTA dose approximately 12 hours apart with or without food. (2.1)
- INLYTA should be swallowed whole with a glass of water. (2.1)
- See Full Prescribing Information for dosage modifications for adverse reactions. (2.2)
- If a strong CYP3A4/5 inhibitor is required, decrease the INLYTA dose by approximately half. (2.2)
- For patients with moderate hepatic impairment, decrease the starting dose by approximately half. (2.2)

3 DOSAGE FORMS AND STRENGTHS

1 mg and 5 mg tablets (3)

4 CONTRAINDICATIONS

None. (4)

5 WARNINGS AND PRECAUTIONS

- Hypertension: Hypertension including hypertensive crisis has been observed. Blood pressure should be well-controlled prior to initiating INLYTA. Monitor for hypertension and treat as needed. Withhold and then dose reduce INLYTA or permanently discontinue based on severity of hypertension. (5.1)
- Arterial and Venous Thromboembolic Events: Arterial and venous thrombotic events have been observed and can be fatal. Use with caution in patients who are at increased risk for these events. Permanently discontinue INLYTA if an arterial thromboembolic event occurs during treatment. Withhold INLYTA and then resume at same dose or permanently discontinue based on severity of VTE. (5.2, 5.3)
- Hemorrhage: Hemorrhagic events, including fatal events, have been reported. INLYTA has not been studied in patients with evidence of untreated brain metastasis or recent active gastrointestinal bleeding and should not be used in those patients. Withhold and then dose reduce INLYTA or discontinue based on severity and persistence of hemorrhage. (5.4)
- Cardiac Failure: Cardiac failure has been observed and can be fatal. Monitor for signs or symptoms of cardiac failure throughout treatment with INLYTA. Management of cardiac failure may require dose reduction, dose interruption or permanent discontinuation of INLYTA. (5.5)
- Gastrointestinal Perforation and Fistula Formation: Gastrointestinal perforation and fistula, including death, have occurred. Use with caution in patients at risk for gastrointestinal perforation or fistula. (5.6)
- Hypothyroidism: Hypothyroidism requiring thyroid hormone replacement has been reported. Monitor thyroid function before initiation of, and periodically throughout, treatment with INLYTA. (5.7)
- Impaired Wound Healing: Withhold INLYTA for at least 2 days prior to elective surgery. Do not administer for at least 2 weeks following major surgery and until adequate wound healing. Resume INLYTA at a reduced dose or discontinue based on severity and persistence of the impaired wound healing. The safety of resumption of INLYTA after resolution of wound healing complications has not been established. (5.8)
- Reversible Posterior Leukoencephalopathy Syndrome (RPLS): RPLS has been observed. Permanently discontinue INLYTA if signs or symptoms of RPLS occur. (5.9)
- Proteinuria: Monitor for proteinuria before initiation of, and periodically throughout, treatment with INLYTA. For moderate to severe proteinuria, withhold and then dose reduce INLYTA. (5.10)
- Hepatotoxicity: Liver enzyme elevation has occurred during treatment with INLYTA as a single agent. Monitor ALT, AST and bilirubin before initiation of, and periodically throughout, treatment with INLYTA. When used in combination with avelumab or pembrolizumab, higher frequencies of Grade 3 and 4 ALT and AST elevation may occur. Consider more frequent monitoring of liver enzymes. Withhold INLYTA and avelumab or pembrolizumab, initiate corticosteroid therapy as needed, and/or permanently discontinue the combination for severe or life-threatening hepatotoxicity. (5.11)
- Use in Patients with Hepatic Impairment: Decrease the starting dose of INLYTA if used in patients with moderate hepatic impairment. INLYTA has not been studied in patients with severe hepatic impairment. (2.2, 5.12)
- Major adverse cardiovascular events (INLYTA in combination with avelumab): Optimize management of cardiovascular risk factors. Permanently discontinue INLYTA in combination with avelumab for Grade 3–4 events. (5.13)
- Embryo-Fetal Toxicity: INLYTA can cause fetal harm. Advise patients of the potential risk to the fetus and to use effective contraception. (5.14, 8.1, 8.3)

6 ADVERSE REACTIONS

Most common adverse reactions (≥20%) are:

INLYTA in combination with avelumab: diarrhea, fatigue, hypertension, musculoskeletal pain, nausea, mucositis, palmar-plantar erythrodysesthesia, dysphonia, decreased appetite, hypothyroidism, rash, hepatotoxicity, cough, dyspnea, abdominal pain, and headache. (6.1)

INLYTA in combination with pembrolizumab: diarrhea, fatigue/asthenia, hypertension, hepatotoxicity, hypothyroidism, decreased appetite, palmar-plantar erythrodysesthesia, nausea, stomatitis/mucosal inflammation, dysphonia, rash, cough, and constipation. (6.1)

INLYTA as a single agent: diarrhea, hypertension, fatigue, decreased appetite, nausea, dysphonia, palmar-plantar erythrodysesthesia (hand-foot) syndrome, weight decreased, vomiting, asthenia, and constipation. (6.1)
To report SUSPECTED ADVERSE REACTIONS, contact Pfizer Inc. at 1-800-438-1985 or FDA at 1-800-FDA-1088 or www.fda.gov/medwatch.

7 DRUG INTERACTIONS

- Avoid strong CYP3A4/5 inhibitors. If unavoidable, reduce the INLYTA dose. (2.2, 7.1)
- Avoid strong CYP3A4/5 inducers. (7.2)

8 USE IN SPECIFIC POPULATIONS

Lactation: Advise not to breastfeed. (8.2)

FULL PRESCRIBING INFORMATION

1 INDICATIONS AND USAGE

1.1 First-Line Advanced Renal Cell Carcinoma

INLYTA in combination with avelumab is indicated for the first-line treatment of patients with advanced renal cell carcinoma (RCC).

INLYTA in combination with pembrolizumab is indicated for the first-line treatment of patients with advanced RCC.

1.2 Second-Line Advanced Renal Cell Carcinoma

INLYTA as a single agent is indicated for the treatment of advanced RCC after failure of one prior systemic therapy.

2 DOSAGE AND ADMINISTRATION

2.1 Recommended Dosing

First-Line Advanced RCC

INLYTA in Combination with Avelumab

The recommended starting dosage of INLYTA is 5 mg orally taken twice daily (12 hours apart) with or without food in combination with avelumab 800 mg administered as an intravenous infusion over 60 minutes every 2 weeks until disease progression or unacceptable toxicity. When INLYTA is used in combination with avelumab, dose escalation of INLYTA above the initial 5 mg dose may be considered at intervals of two weeks or longer. Review the Full Prescribing Information for recommended avelumab dosing information.

INLYTA in Combination with Pembrolizumab

The recommended starting dosage of INLYTA is 5 mg orally twice daily (12 hours apart) with or without food in combination with pembrolizumab 200 mg every 3 weeks or 400 mg every 6 weeks administered as an intravenous infusion over 30 minutes until disease progression or unacceptable toxicity. When INLYTA is used in combination with pembrolizumab, dose escalation of INLYTA above the initial 5 mg dose may be considered at intervals of six weeks or longer. Review the Full Prescribing Information for recommended pembrolizumab dosing information.

Second-Line Advanced RCC

When INLYTA is used as a single agent, the recommended starting oral dose is 5 mg twice daily. Administer INLYTA doses approximately 12 hours apart with or without food.

Important Administration Instructions

Advise patients to swallow INLYTA whole with a full glass of water. If the patient vomits or misses a dose, an additional dose should not be taken. Advise the patient to take the next prescribed dose at the usual time.

2.2 Dose Modification Guidelines

Dose increase or reduction is recommended based on individual safety and tolerability.

Recommended INLYTA dosage increases and reductions are provided in Table 1.

Over the course of treatment, patients who tolerate INLYTA for at least two consecutive weeks with no adverse reactions Grade >2 (according to the Common Toxicity Criteria for Adverse Events [CTCAE]), are normotensive, and are not receiving anti-hypertension medication, may have their dose increased.

Table 1: Recommended Dosage Increases and Reductions for INLYTA
Dose Modification | Dose Regimen
Recommended starting dosage | 5 mg twice daily
Dosage increase
First dose increase | 7 mg twice daily
Second dose increase | 10 mg twice daily
Dosage reduction [for management of adverse drug reactions]
First dose reduction [from 5 mg twice daily] | 3 mg twice daily
Second dose reduction | 2 mg twice daily

Recommended dosage modifications for adverse reactions for INLYTA are provided in Table 2.

Table 2: Recommended Dosage Modification for INLYTA for Adverse Reactions
Adverse Reaction | Severity | Dosage Modifications for INLYTA
Hypertension [see Warnings and Precautions (5.1)] | SBP >150 mmHg or DBP >100 mmHg despite antihypertensive treatment | - Reduce dose by one level.
Hypertension [see Warnings and Precautions (5.1)] | SBP >160 mmHg or DBP >105 mmHg | - Withhold until BP <150/100 mmHg. - Resume at a reduced dose.
Hypertension [see Warnings and Precautions (5.1)] | Grade 4 or hypertensive crisis | - Permanently discontinue.
Hemorrhage [see Warnings and Precautions (5.4)] | Grade 3 or 4 | - Withhold until resolution to Grade 0 or 1 or baseline. - Either resume at a reduced dose or discontinue depending on the severity and persistence of adverse reaction.
Cardiac failure [see Warnings and Precautions (5.5)] | Asymptomatic cardiomyopathy (left ventricular ejection fraction greater than 20% but less than 50% below baseline or below the lower limit of normal if baseline was not obtained) | - Withhold until resolution to Grade 0 or 1 or baseline. - Resume at a reduced dose.
 | Clinically manifested congestive heart failure | - Permanently discontinue.
Impaired wound healing [see Warnings and Precautions (5.8)] | Any Grade | - The safety of resumption of INLYTA after resolution of wound healing has not been established. - Either resume at a reduced dose or discontinue depending on the severity and persistence of the adverse reaction.
Reversible Posterior Leukoencephalopathy Syndrome [see Warnings and Precautions (5.9)] | Any Grade | - Permanently discontinue.
Proteinuria [see Warnings and Precautions (5.10)] | 2 or more grams proteinuria per 24 hours | - Withhold until resolution to less than 2 grams per 24 hours. - Resume at a reduced dose.
Other Adverse Reactions | Grade 3 | - Reduce dosage by one level.
 | Grade 4 | - Withhold until resolution to Grade 2. - Resume at a reduced dose.

Table 3 represents additional recommended dosage modifications for adverse reactions when INLYTA is administered in combination with avelumab or pembrolizumab.

See the Full Prescribing Information for additional dosage information for avelumab or pembrolizumab including dose modifications for immune-mediated adverse reactions.

Table 3: Recommended Dosage Modification for Adverse Reactions for INLYTA in Combination with Avelumab or Pembrolizumab
Treatment | Adverse Reaction | Severity [Based on Common Terminology Criteria for Adverse Events (CTCAE), version 4.0.] | Dosage Modifications for INLYTA
INLYTA in combination with avelumab OR pembrolizumab | Liver enzyme elevations [Consider corticosteroid therapy] | ALT or AST at least 3 times ULN but less than 10 times ULN without concurrent total bilirubin at least 2 times ULN | - Withhold both INLYTA and avelumab or pembrolizumab until resolution to Grades 0–1 - Consider rechallenge with INLYTA and/or avelumab or pembrolizumab [If rechallenging with INLYTA, consider dosage reduction per Table 1. Consider rechallenge with a single drug or sequential rechallenge with both drugs after recovery.]
INLYTA in combination with avelumab OR pembrolizumab | Liver enzyme elevations [Consider corticosteroid therapy] | ALT or AST increases to more than 3 times ULN with concurrent total bilirubin at least 2 times ULN or ALT or AST at least 10 times ULN | - Permanently discontinue both INLYTA and avelumab or pembrolizumab
INLYTA in combination with avelumab OR pembrolizumab | Diarrhea | Grade 1–2 | - Initiate symptomatic medications.
INLYTA in combination with avelumab OR pembrolizumab | Diarrhea | Grade 3 | - Interrupt INLYTA and initiate symptomatic medications. If diarrhea is controlled, INLYTA may be resumed at either the same dose or reduced by 1 dose level.
INLYTA in combination with avelumab OR pembrolizumab | Diarrhea | Grade 4 | - Withhold INLYTA until resolution to Grade <2, then restart INLYTA dose reduced by 1 dose level
INLYTA in combination with avelumab | Major Adverse Cardiovascular Events (MACE) | Grade 3 or 4 | - Permanently discontinue
ALT = alanine aminotransferase, AST = aspartate aminotransferase, ULN = upper limit normal

2.3 Dosage Modification for Drug Interactions

Strong CYP3A4/5 Inhibitors

The concomitant use of strong CYP3A4/5 inhibitors should be avoided (e.g., ketoconazole, itraconazole, clarithromycin, atazanavir, indinavir, nefazodone, nelfinavir, ritonavir, saquinavir, telithromycin, and voriconazole). Selection of an alternate concomitant medication with no or minimal CYP3A4/5 inhibition potential is recommended. Although INLYTA dose adjustment has not been studied in patients receiving strong CYP3A4/5 inhibitors, if a strong CYP3A4/5 inhibitor must be co-administered, a dose decrease of INLYTA by approximately half is recommended, as this dose reduction is predicted to adjust the axitinib area under the plasma concentration vs time curve (AUC) to the range observed without inhibitors. The subsequent doses can be increased or decreased based on individual safety and tolerability. If co-administration of the strong inhibitor is discontinued, the INLYTA dose should be returned (after 3 – 5 half-lives of the inhibitor) to that used prior to initiation of the strong CYP3A4/5 inhibitor [see Drug Interactions (7.1) and Clinical Pharmacology (12.3)].

2.4 Dosage Modification for Hepatic Impairment

No starting dose adjustment is required when administering INLYTA to patients with mild hepatic impairment (Child-Pugh class A). Based on the pharmacokinetic data, the INLYTA starting dose should be reduced by approximately half in patients with baseline moderate hepatic impairment (Child-Pugh class B). The subsequent doses can be increased or decreased based on individual safety and tolerability. INLYTA has not been studied in patients with severe hepatic impairment (Child-Pugh class C) [see Warnings and Precautions (5.12), Use in Specific Populations (8.6), and Clinical Pharmacology (12.3)].

3 DOSAGE FORMS AND STRENGTHS

- 1 mg tablets of INLYTA: red, film-coated, oval tablets, debossed with "Pfizer" on one side and "1 XNB" on the other side.
- 5 mg tablets of INLYTA: red, film-coated, triangular tablets, debossed with "Pfizer" on one side and "5 XNB" on the other side.

4 CONTRAINDICATIONS

None.

5 WARNINGS AND PRECAUTIONS

5.1 Hypertension

In a controlled clinical study with INLYTA for the treatment of patients with RCC, hypertension was reported in 145/359 patients (40%) receiving INLYTA and 103/355 patients (29%) receiving sorafenib. Grade 3/4 hypertension was observed in 56/359 patients (16%) receiving INLYTA and 39/355 patients (11%) receiving sorafenib. Hypertensive crisis was reported in 2/359 patients (<1%) receiving INLYTA and none of the patients receiving sorafenib. The median onset time for hypertension (systolic blood pressure >150 mmHg or diastolic blood pressure >100 mmHg) was within the first month of the start of INLYTA treatment and blood pressure increases have been observed as early as 4 days after starting INLYTA. Hypertension was managed with standard anti-hypertensive therapy. Discontinuation of INLYTA treatment due to hypertension occurred in 1/359 patients (<1%) receiving INLYTA and none of the patients receiving sorafenib [see Adverse Reactions (6.1)].

Ensure that blood pressure is well-controlled prior to initiating INLYTA. Monitor patients for hypertension and treat as needed with standard anti-hypertensive therapy. Withhold and then dose reduce INLYTA or permanently discontinue based on severity of hypertension [see Dosage and Administration (2.2)].

5.2 Arterial Thromboembolic Events

In clinical trials, arterial thromboembolic events have been reported, including deaths. In a controlled clinical study with INLYTA for the treatment of patients with RCC, Grade 3/4 arterial thromboembolic events were reported in 4/359 patients (1%) receiving INLYTA and 4/355 patients (1%) receiving sorafenib. Fatal cerebrovascular accident was reported in 1/359 patients (<1%) receiving INLYTA and none of the patients receiving sorafenib [see Adverse Reactions (6.1)].

INLYTA has not been studied in patients who had an arterial thromboembolic event within the previous 12 months. In clinical trials with INLYTA, arterial thromboembolic events (including transient ischemic attack, cerebrovascular accident, myocardial infarction, and retinal artery occlusion) were reported in 17/715 patients (2%), with two deaths secondary to cerebrovascular accident.

Permanently discontinue INLYTA if an arterial thromboembolic event occurs during treatment.

5.3 Venous Thromboembolic Events

In clinical trials, venous thromboembolic events have been reported, including deaths. In a controlled clinical study with INLYTA for the treatment of patients with RCC, venous thromboembolic events were reported in 11/359 patients (3%) receiving INLYTA and 2/355 patients (1%) receiving sorafenib. Grade 3/4 venous thromboembolic events were reported in 9/359 patients (3%) receiving INLYTA (including pulmonary embolism, deep vein thrombosis, retinal vein occlusion and retinal vein thrombosis) and 2/355 patients (1%) receiving sorafenib. Fatal pulmonary embolism was reported in 1/359 patients (<1%) receiving INLYTA and none of the patients receiving sorafenib.

INLYTA has not been studied in patients who had a venous thromboembolic event within the previous 6 months. In clinical trials with INLYTA, venous thromboembolic events were reported in 22/715 patients (3%), with two deaths secondary to pulmonary embolism.

Monitor for signs and symptoms of VTE and PE. Withhold INLYTA and then resume at same dose or permanently discontinue based on severity of VTE.

5.4 Hemorrhage

In a controlled clinical study with INLYTA for the treatment of patients with RCC, hemorrhagic events were reported in 58/359 patients (16%) receiving INLYTA and 64/355 patients (18%) receiving sorafenib. Grade 3/4 hemorrhagic events were reported in 5/359 (1%) patients receiving INLYTA (including cerebral hemorrhage, hematuria, hemoptysis, lower gastrointestinal hemorrhage, and melena) and 11/355 (3%) patients receiving sorafenib. Fatal hemorrhage was reported in 1/359 patients (<1%) receiving INLYTA (gastric hemorrhage) and 3/355 patients (1%) receiving sorafenib.

INLYTA has not been studied in patients who have evidence of untreated brain metastasis or recent active gastrointestinal bleeding and should not be used in those patients. Withhold and then dose reduce INLYTA or discontinue based on severity and persistence of hemorrhage.

5.5 Cardiac Failure

In a controlled clinical study with INLYTA for the treatment of patients with RCC, cardiac failure was reported in 6/359 patients (2%) receiving INLYTA and 3/355 patients (1%) receiving sorafenib. Grade 3/4 cardiac failure was observed in 2/359 patients (1%) receiving INLYTA and 1/355 patients (<1%) receiving sorafenib. Fatal cardiac failure was reported in 2/359 patients (1%) receiving INLYTA and 1/355 patients (<1%) receiving sorafenib. Monitor for signs or symptoms of cardiac failure throughout treatment with INLYTA. Management of cardiac failure may require dose reduction, dose interruption or permanent discontinuation of INLYTA [see Dosage and Administration (2.2)].

5.6 Gastrointestinal Perforation and Fistula Formation

In a controlled clinical study with INLYTA for the treatment of patients with RCC, gastrointestinal perforation was reported in 1/359 patients (<1%) receiving INLYTA and none of the patients receiving sorafenib. In clinical trials with INLYTA, gastrointestinal perforation was reported in 5/715 patients (1%), including one death. In addition to cases of gastrointestinal perforation, fistulas were reported in 4/715 patients (1%).

Monitor for symptoms of gastrointestinal perforation or fistula periodically throughout treatment with INLYTA.

5.7 Thyroid Dysfunction

In a controlled clinical study with INLYTA for the treatment of patients with RCC, hypothyroidism was reported in 69/359 patients (19%) receiving INLYTA and 29/355 patients (8%) receiving sorafenib. Hyperthyroidism was reported in 4/359 patients (1%) receiving INLYTA and 4/355 patients (1%) receiving sorafenib. In patients who had thyroid stimulating hormone (TSH) <5 μU/mL before treatment, elevations of TSH to ≥10 μU/mL occurred in 79/245 patients (32%) receiving INLYTA and 25/232 patients (11%) receiving sorafenib [see Adverse Reactions (6.1)].

Monitor thyroid function before initiation of, and periodically throughout, treatment with INLYTA. Treat hypothyroidism and hyperthyroidism according to standard medical practice to maintain euthyroid state.

5.8 Impaired Wound Healing

Impaired wound healing can occur in patients who receive drugs that inhibit the vascular endothelial growth factor (VEGF) signaling pathway. Therefore, INLYTA has the potential to adversely affect wound healing.

Withhold INLYTA for at least 2 days prior to elective surgery. Do not administer for at least 2 weeks following major surgery and until adequate wound healing. Resume INLYTA at a reduced dose or discontinue based on severity and persistence of the impaired wound healing. The safety of resumption of INLYTA after resolution of wound healing complications has not been established [see Dosage and Administration (2.2)].

5.9 Reversible Posterior Leukoencephalopathy Syndrome

In a controlled clinical study with INLYTA for the treatment of patients with RCC, reversible posterior leukoencephalopathy syndrome (RPLS) was reported in 1/359 patients (<1%) receiving INLYTA and none of the patients receiving sorafenib [see Adverse Reactions (6.1)]. There were two additional reports of RPLS in other clinical trials with INLYTA.

RPLS is a neurological disorder which can present with headache, seizure, lethargy, confusion, blindness and other visual and neurologic disturbances. Mild to severe hypertension may be present. Magnetic resonance imaging is necessary to confirm the diagnosis of RPLS. Permanently discontinue INLYTA in patients developing RPLS. The safety of reinitiating INLYTA therapy in patients previously experiencing RPLS is not known [see Dosage and Administration (2.2)].

5.10 Proteinuria

In a controlled clinical study with INLYTA for the treatment of patients with RCC, proteinuria was reported in 39/359 patients (11%) receiving INLYTA and 26/355 patients (7%) receiving sorafenib. Grade 3 proteinuria was reported in 11/359 patients (3%) receiving INLYTA and 6/355 patients (2%) receiving sorafenib [see Adverse Reactions (6.1)].

Monitoring for proteinuria before initiation of, and periodically throughout, treatment with INLYTA is recommended. For patients who develop moderate to severe proteinuria, withhold and then dose reduce INLYTA [see Dosage and Administration (2.2)].

5.11 Hepatotoxicity

INLYTA as a Single Agent

In a controlled clinical study with INLYTA for the treatment of patients with RCC, alanine aminotransferase (ALT) elevations of all grades occurred in 22% of patients on both arms, with Grade 3/4 events in <1% of patients on the INLYTA arm. When used as a single agent, monitor ALT, aspartate aminotransferase (AST) and bilirubin before initiation of and periodically throughout treatment with INLYTA.

INLYTA in Combination with Avelumab or with Pembrolizumab

INLYTA in combination with avelumab or with pembrolizumab can cause hepatotoxicity with higher than expected frequencies of Grade 3 and 4 ALT and AST elevations. Monitor liver enzymes before initiation of and periodically throughout treatment. Consider more frequent monitoring of liver enzymes as compared to when the drugs are administered as single agents. For elevated liver enzymes, interrupt or permanently discontinue INLYTA and avelumab or pembrolizumab, and administer corticosteroids as needed [see Dosage and Administration (2.3)].

With the combination of INLYTA and avelumab, Grades 3 and 4 increased ALT and increased AST were reported in 9% and 7% of patients, respectively. In patients with ALT ≥3 times ULN (Grades 2–4, n=82), ALT resolved to Grades 0–1 in 92%. Among the 73 patients who were rechallenged with either avelumab (n=3) or axitinib (n=25) administered as a single agent or with both (n=45), recurrence of ALT ≥3 times ULN was observed in no patient receiving avelumab, 6 patients receiving INLYTA, and 15 patients receiving both avelumab and INLYTA. Twenty-two (88%) patients with a recurrence of ALT ≥3 ULN subsequently recovered to Grade 0–1 from the event. Immune-mediated hepatitis was reported in 7% of patients including 4.9% with Grade 3 or 4 immune-mediated hepatitis. Hepatotoxicity led to permanent discontinuation in 7% and immune-mediated hepatitis led to permanent discontinuation of either avelumab or INLYTA in 5% of patients. Thirty-four patients were treated with corticosteroids and one patient was treated with a non-steroidal immunosuppressant. Resolution of hepatitis occurred in 31 of the 35 patients at the time of data cut-off.

With the combination of INLYTA and pembrolizumab, Grades 3 and 4 increased ALT (20%) and increased AST (13%) were seen. Fifty-nine percent of the patients with increased ALT received systemic corticosteroids. In patients with ALT ≥3 times ULN (Grades 2–4, n=116), ALT resolved to Grades 0–1 in 94%. Among the 92 patients who were rechallenged with either pembrolizumab (n=3) or INLYTA (n=34) administered as a single agent or with both (n=55), recurrence of ALT ≥3 times ULN was observed in 1 patient receiving pembrolizumab, 16 patients receiving INLYTA, and 24 patients receiving both pembrolizumab and INLYTA. All patients with a recurrence of ALT ≥3 ULN subsequently recovered from the event.

5.12 Use in Patients with Hepatic Impairment

The systemic exposure to axitinib was higher in subjects with moderate hepatic impairment (Child-Pugh class B) compared to subjects with normal hepatic function. A dose decrease is recommended when administering INLYTA to patients with moderate hepatic impairment (Child-Pugh class B). INLYTA has not been studied in patients with severe hepatic impairment (Child-Pugh class C) [see Dosage and Administration (2.2), Use in Specific Populations (8.6), and Clinical Pharmacology (12.3)].

5.13 Major Adverse Cardiovascular Events (MACE)

INLYTA in combination with avelumab can cause severe and fatal cardiovascular events. Consider baseline and periodic evaluations of left ventricular ejection fraction. Monitor for signs and symptoms of cardiovascular events. Optimize management of cardiovascular risk factors, such as hypertension, diabetes, or dyslipidemia. Permanently discontinue INLYTA and avelumab for Grade 3–4 cardiovascular events.

MACE occurred in 7% of patients with advanced RCC treated with INLYTA in combination with avelumab compared to 3.4% treated with sunitinib in a randomized trial, JAVELIN Renal 101. These events included death due to cardiac events (1.4%), Grade 3–4 myocardial infarction (2.8%), and Grade 3–4 congestive heart failure (1.8%). Median time to onset of MACE was 4.2 months (range: 2 days to 24.5 months).

5.14 Embryo-Fetal Toxicity

Based on its mechanism of action and findings from animal studies, INLYTA can cause fetal harm when administered to a pregnant woman. There are no available human data to inform the drug-associated risk. In developmental toxicity studies in mice, axitinib was teratogenic, embryotoxic and fetotoxic at maternal exposures that were lower than human exposures at the recommended clinical dose. Advise females of reproductive potential of the potential risk to the fetus and to use effective contraception during treatment with INLYTA and for 1 week after the last dose. Advise males with female partners of reproductive potential to use effective contraception during treatment with INLYTA and for 1 week after the last dose [see Use in Specific Populations (8.1, 8.3), Clinical Pharmacology (12.1)].

When INLYTA is used in combination with avelumab or pembrolizumab, refer to the full prescribing information of avelumab or pembrolizumab for pregnancy and contraception information.

6 ADVERSE REACTIONS

The following clinically significant adverse reactions are discussed elsewhere in the labeling [see Warnings and Precautions (5)]:

- Hypertension [see Warnings and Precautions (5.1)]
- Arterial thromboembolic events [see Warnings and Precautions (5.2)]
- Venous thromboembolic events [see Warnings and Precautions (5.3)]
- Hemorrhage [see Warnings and Precautions (5.4)]
- Cardiac failure [see Warnings and Precautions (5.5)]
- Gastrointestinal perforation and fistula formation [see Warnings and Precautions (5.6)]
- Thyroid dysfunction [see Warnings and Precautions (5.7)]
- Reversible posterior leukoencephalopathy syndrome [see Warnings and Precautions (5.9)]
- Proteinuria [see Warnings and Precautions (5.10)]
- Hepatotoxicity [see Warnings and Precautions (5.11)]
- Hepatic impairment [see Warnings and Precautions (5.12)]

6.1 Clinical Trials Experience

Because clinical trials are conducted under widely varying conditions, adverse reaction rates observed in the clinical trials of a drug cannot be directly compared to rates in the clinical trials of another drug and may not reflect the rates observed in clinical practice.

The safety of INLYTA has been evaluated in combination with avelumab in JAVELIN Renal 101 and pembrolizumab in KEYNOTE-426 for the first-line treatment of patients with advanced RCC [see Clinical Studies (14.1)]. The data described [see Adverse Reactions (6.1)] reflect exposure to INLYTA in combination with avelumab in 434 patients and pembrolizumab in 429 patients [see Clinical Studies (14.1)].

The safety of INLYTA has been evaluated in 715 patients in second-line monotherapy studies, which included 537 patients with advanced RCC. The data described [see Adverse Reactions (6.1)] reflect exposure to INLYTA in 359 patients with advanced RCC who participated in a randomized clinical study versus sorafenib [see Clinical Studies (14.2)].

First-Line Advanced RCC

INLYTA in Combination with Avelumab

The safety of INLYTA in combination with avelumab was evaluated in JAVELIN Renal 101. Patients with autoimmune disease other than type I diabetes mellitus, vitiligo, psoriasis, or thyroid disorders not requiring immunosuppressive treatment were excluded. Patients received INLYTA 5 mg twice daily (N=434) in combination with avelumab 10 mg/kg every 2 weeks administered or sunitinib 50 mg once daily for 4 weeks followed by 2 weeks off (N=439).

In the INLYTA plus avelumab arm, 70% were exposed to avelumab for ≥6 months and 29% were exposed for ≥1 year in JAVELIN Renal 101 [see Clinical Studies (14.1)].

The median age of patients treated with INLYTA in combination with avelumab was 62 years (range: 29 to 83), 38% of patients were 65 years or older, 71% were male, 75% were White, and the Eastern Cooperative Oncology Group (ECOG) performance score was 0 (64%) or 1 (36%).

Fatal adverse reactions occurred in 1.8% of patients receiving INLYTA in combination with avelumab. These included sudden cardiac death (1.2%), stroke (0.2%), myocarditis (0.2%), and necrotizing pancreatitis (0.2%).

Serious adverse reactions occurred in 35% of patients receiving INLYTA in combination with avelumab. Serious adverse reactions in ≥1% of patients included diarrhea (2.5%), dyspnea (1.8%), hepatotoxicity (1.8%), venous thromboembolic disease (1.6%), acute kidney injury (1.4%), and pneumonia (1.2%).

Permanent discontinuation due to an adverse reaction of either INLYTA or avelumab occurred in 22% of patients: 19% avelumab only, 13% INLYTA only, and 8% both drugs. The most common adverse reactions (>1%) resulting in permanent discontinuation of avelumab or the combination were hepatotoxicity (6%) and infusion-related reaction (1.8%).

Dose interruptions or reductions due to an adverse reaction, excluding temporary interruptions of avelumab infusions due to infusion-related reactions, occurred in 76% of patients receiving INLYTA in combination with avelumab. This includes interruption of avelumab in 50% of patients. INLYTA was interrupted in 66% and dose reduced in 19% of patients. The most common adverse reaction (>10%) resulting in interruption of avelumab was diarrhea (10%). The most common adverse reactions resulting in either interruption or dose reduction of INLYTA were diarrhea (19%), hypertension (18%), palmar-plantar erythrodysesthesia (18%), and hepatotoxicity (10%).

The most common adverse reactions (≥20%) in patients receiving INLYTA in combination with avelumab were diarrhea, fatigue, hypertension, musculoskeletal pain, nausea, mucositis, palmar-plantar erythrodysesthesia, dysphonia, decreased appetite, hypothyroidism, rash, hepatotoxicity, cough, dyspnea, abdominal pain, and headache.

Forty-eight (11%) of patients treated with INLYTA in combination with avelumab received an oral prednisone dose equivalent to ≥40 mg daily for an immune-mediated adverse reaction [see Warnings and Precautions (5.12)].

Table 4 summarizes adverse reactions that occurred in ≥20% of INLYTA in combination with avelumab-treated patients.

Table 4: Adverse Reactions (≥20%) of Patients Receiving INLYTA in Combination with Avelumab (JAVELIN Renal 101 Trial) [The trial was not designed to demonstrate a statistically significant difference in the incidence of adverse reactions between avelumab in combination with INLYTA and sunitinib.]
Adverse Reactions | INLYTA plus Avelumab (N=434) |  | Sunitinib (N=439)
 | All Grades % | Grade 3–4 % | All Grades % | Grade 3–4 %
Gastrointestinal Disorders
Diarrhea [Diarrhea is a composite term that includes diarrhea, autoimmune colitis, and colitis] | 62 | 8 | 48 | 2.7
Nausea | 34 | 1.4 | 39 | 1.6
Mucositis [Mucositis is a composite term that includes mucosal inflammation and stomatitis] | 34 | 2.8 | 35 | 2.1
Hepatotoxicity [Hepatotoxicity is a composite term that includes ALT increased, AST increased, autoimmune hepatitis, bilirubin conjugated, bilirubin conjugated increased, blood bilirubin increased, drug-induced liver injury, hepatic enzyme increased, hepatic function abnormal, hepatitis, hepatitis fulminant, hepatocellular injury, hepatotoxicity, hyperbilirubinemia, immune-mediated hepatitis, liver function test increased, liver disorder, liver injury, and transaminases increased] | 24 | 9 | 18 | 3.6
Abdominal pain [Abdominal pain is a composite term that includes abdominal pain, flank pain, abdominal pain upper, and abdominal pain lower] | 22 | 1.4 | 19 | 2.1
General Disorders and Administration Site Conditions
Fatigue [Fatigue is a composite term that includes fatigue and asthenia] | 53 | 6 | 54 | 6
Vascular Disorders
Hypertension [Hypertension is a composite term that includes hypertension and hypertensive crisis] | 50 | 26 | 36 | 17
Musculoskeletal and Connective Tissue Disorders
Musculoskeletal pain [Musculoskeletal pain is a composite term that includes musculoskeletal pain, musculoskeletal chest pain, myalgia, back pain, bone pain, musculoskeletal discomfort, neck pain, spinal pain, and pain in extremity] | 40 | 3.2 | 33 | 2.7
Skin and Subcutaneous Tissue Disorders
Palmar-plantar erythrodysesthesia | 33 | 6 | 34 | 4
Rash [Rash is a composite term that includes rash, rash generalized, rash macular, rash maculo-papular, rash pruritic, rash erythematous, rash papular, and rash pustular] | 25 | 0.9 | 16 | 0.5
Respiratory, Thoracic and Mediastinal Disorders
Dysphonia | 31 | 0.5 | 3.2 | 0
Dyspnea [Dyspnea is a composite term that includes dyspnea, dyspnea exertional and dyspnea at rest] | 23 | 3.0 | 16 | 1.8
Cough | 23 | 0.2 | 19 | 0
Metabolism and Nutrition Disorders
Decreased appetite | 26 | 2.1 | 29 | 0.9
Endocrine Disorders
Hypothyroidism | 25 | 0.2 | 14 | 0.2
Nervous System Disorders
Headache | 21 | 0.2 | 16 | 0.2
Toxicity was graded per National Cancer Institute Common Terminology Criteria for Adverse Events. Version 4.03 (NCI CTCAE v4).

Other clinically important adverse reactions that occurred in less than 20% of patients in JAVELIN Renal 101 included arthralgia, weight decreased, and chills.

Patients received pre-medication with an anti-histamine and acetaminophen prior to each infusion. Infusion-related reactions occurred in 12% (Grade 3: 1.6%; no Grade 4) of patients treated with INLYTA in combination with avelumab.

Table 5 summarizes selected laboratory abnormalities that occurred in ≥20% of INLYTA in combination with avelumab-treated patients.

Table 5: Selected Laboratory Abnormalities Worsening from Baseline Occurring in ≥20% of Patients Receiving INLYTA in Combination with Avelumab (JAVELIN Renal 101 Trial) [The trial was not designed to demonstrate a statistically significant difference in the incidence of laboratory abnormalities between INLYTA in combination with avelumab and sunitinib.]
Laboratory Abnormality | INLYTA plus Avelumab |  | Sunitinib [Each test incidence is based on the number of patients who had both baseline and at least one on-study laboratory measurement available: INLYTA in combination with avelumab group (range: 413 to 428 patients) and sunitinib group (range: 405 to 433 patients).]
 | Any Grade % | Grade 3–4 % | Any Grade % | Grade 3–4 %
Chemistry
Blood triglycerides increased | 71 | 13 | 48 | 5
Blood creatinine increased | 62 | 2.3 | 68 | 1.4
Blood cholesterol increased | 57 | 1.9 | 22 | 0.7
Alanine aminotransferase increased (ALT) | 50 | 9 | 46 | 3.2
Aspartate aminotransferase increased (AST) | 47 | 7 | 57 | 3.2
Blood sodium decreased | 38 | 9 | 37 | 10
Lipase increased | 37 | 14 | 25 | 7
Blood potassium increased | 35 | 3.0 | 28 | 3.9
Blood bilirubin increased | 21 | 1.4 | 23 | 1.4
Hematology
Platelet count decreased | 27 | 0.7 | 80 | 1.5
Hemoglobin decreased | 21 | 2.1 | 65 | 8

INLYTA in Combination with Pembrolizumab

The safety of INLYTA in combination with pembrolizumab was investigated in KEYNOTE-426 [see Clinical Studies (14.1)]. Patients with medical conditions that required systemic corticosteroids or other immunosuppressive medications or had a history of severe autoimmune disease other than type 1 diabetes, vitiligo, Sjogren's syndrome, and hypothyroidism stable on hormone replacement were ineligible. Patients received INLYTA 5 mg orally twice daily and pembrolizumab 200 mg intravenously every 3 weeks, or sunitinib 50 mg once daily for 4 weeks and then off treatment for 2 weeks. The median duration of exposure to the combination therapy of INLYTA and pembrolizumab was 10.4 months (range: 1 day to 21.2 months).

The study population characteristics were: median age of 62 years (range: 30 to 89), 40% age 65 or older; 71% male; 80% White; and 80% Karnofsky Performance Status (KPS) of 90–100 and 20% KPS of 70–80.

Fatal adverse reactions occurred in 3.3% of patients receiving INLYTA in combination with pembrolizumab. These included 3 cases of cardiac arrest, 2 cases of pulmonary embolism and 1 case each of cardiac failure, death due to unknown cause, myasthenia gravis, myocarditis, Fournier's gangrene, plasma cell myeloma, pleural effusion, pneumonitis, and respiratory failure.

Serious adverse reactions occurred in 40% of patients receiving INLYTA in combination with pembrolizumab. Serious adverse reactions in ≥1% of patients receiving INLYTA in combination with pembrolizumab included hepatotoxicity (7%), diarrhea (4.2%), acute kidney injury (2.3%), dehydration (1%), and pneumonitis (1%).

Permanent discontinuation due to an adverse reaction of either INLYTA or pembrolizumab occurred in 31% of patients; 13% pembrolizumab only, 13% INLYTA only, and 8% both drugs. The most common adverse reaction (>1%) resulting in permanent discontinuation of INLYTA, pembrolizumab, or the combination was hepatotoxicity (13%), diarrhea/colitis (1.9%), acute kidney injury (1.6%), and cerebrovascular accident (1.2%).

Dose interruptions or reductions due to an adverse reaction, excluding temporary interruptions of pembrolizumab infusions due to infusion-related reactions, occurred in 76% of patients receiving pembrolizumab in combination with INLYTA. This includes interruption of pembrolizumab in 50% of patients. INLYTA was interrupted in 64% of patients and dose reduced in 22% of patients. The most common adverse reactions (>10%) resulting in either interruption or reduction of INLYTA were hepatotoxicity (21%), diarrhea (19%), and hypertension (18%) and the most common adverse reactions (>10%) resulting in interruption of pembrolizumab were hepatotoxicity (14%) and diarrhea (11%).

The most common adverse reactions (≥20%) in patients receiving INLYTA and pembrolizumab were diarrhea, fatigue/asthenia, hypertension, hepatotoxicity, hypothyroidism, decreased appetite, palmar-plantar erythrodysesthesia, nausea, stomatitis/mucosal inflammation, dysphonia, rash, cough, and constipation.

Twenty-seven percent (27%) of patients treated with INLYTA in combination with pembrolizumab received an oral prednisone dose equivalent to ≥40 mg daily for an immune-mediated adverse reaction.

Tables 6 and 7 summarize the adverse reactions and laboratory abnormalities, respectively, that occurred in at least 20% of patients treated with INLYTA and pembrolizumab in KEYNOTE-426.

Table 6: Adverse Reactions Occurring in ≥20% of Patients Treated with INLYTA and Pembrolizumab (KEYNOTE-426 Trial)
Adverse Reactions | INLYTA plus Pembrolizumab N=429 |  | Sunitinib N=425
 | All Grades [Graded per NCI CTCAE v4.03] % | Grades 3–4 % | All Grades % | Grades 3–4 %
Gastrointestinal Disorders
Diarrhea [Includes diarrhea, colitis, enterocolitis, gastroenteritis, enteritis, enterocolitis hemorrhagic] | 56 | 11 | 45 | 5
Nausea | 28 | 0.9 | 32 | 0.9
Constipation | 21 | 0 | 15 | 0.2
General
Fatigue/Asthenia | 52 | 5 | 51 | 10
Vascular
Hypertension [Includes hypertension, blood pressure increased, hypertensive crisis, labile hypertension] | 48 | 24 | 48 | 20
Hepatobiliary
Hepatotoxicity [Includes ALT increased, AST increased, autoimmune hepatitis, blood bilirubin increased, drug-induced liver injury, hepatic enzyme increased, hepatic function abnormal, hepatitis, hepatitis fulminant, hepatocellular injury, hepatotoxicity, hyperbilirubinemia, immune-mediated hepatitis, liver function test increased, liver injury, transaminases increased] | 39 | 20 | 25 | 4.9
Endocrine
Hypothyroidism | 35 | 0.2 | 32 | 0.2
Metabolism and Nutrition
Decreased appetite | 30 | 2.8 | 29 | 0.7
Skin and Subcutaneous Tissue
Palmar-plantar erythrodysesthesia syndrome | 28 | 5 | 40 | 3.8
Stomatitis/Mucosal inflammation | 27 | 1.6 | 41 | 4
Rash [Includes rash, butterfly rash, dermatitis, dermatitis acneform, dermatitis atopic, dermatitis, bullous, dermatitis contact, exfoliative rash, genital rash, rash erythematous, rash generalized, rash macular, rash maculopapular, rash papular, rash pruritic, seborrheic dermatitis, skin discoloration, skin exfoliation, perineal rash] | 25 | 1.4 | 21 | 0.7
Respiratory, Thoracic, and Mediastinal
Dysphonia | 25 | 0.2 | 3.3 | 0
Cough | 21 | 0.2 | 14 | 0.5

Table 7: Laboratory Abnormalities Worsened from Baseline Occurring in ≥20% of Patients Receiving INLYTA With Pembrolizumab in KEYNOTE-426
Laboratory Test [Each test incidence is based on the number of patients who had both baseline and at least one on-study laboratory measurement available: pembrolizumab/axitinib (range: 342 to 425 patients) and sunitinib (range: 345 to 422 patients).] | INLYTA plus Pembrolizumab |  | Sunitinib
 | All Grades [Graded per NCI CTCAE v4.03] % | Grade 3–4 % | All Grades % | Grade 3–4 %
Chemistry
Hyperglycemia | 62 | 9 | 54 | 3.2
Increased ALT | 60 | 20 | 44 | 5
Increased AST | 57 | 13 | 56 | 5
Increased creatinine | 43 | 4.3 | 40 | 2.4
Hyponatremia | 35 | 8 | 29 | 8
Hyperkalemia | 34 | 6 | 22 | 1.7
Hypoalbuminemia | 32 | 0.5 | 34 | 1.7
Hypercalcemia | 27 | 0.7 | 15 | 1.9
Hypophosphatemia | 26 | 6 | 49 | 17
Increased alkaline phosphatase | 26 | 1.7 | 30 | 2.7
Hypocalcemia [Corrected for albumin] | 22 | 0.2 | 29 | 0.7
Blood bilirubin increased | 22 | 2.1 | 21 | 1.9
Activated partial thromboplastin time prolonged [Two patients with a Grade 3 elevated activated partial thromboplastin time prolonged (aPTT) were also reported as having an adverse reaction of hepatotoxicity.] | 22 | 1.2 | 14 | 0
Hematology
Lymphopenia | 33 | 11 | 46 | 8
Anemia | 29 | 2.1 | 65 | 8
Thrombocytopenia | 27 | 1.4 | 78 | 14

Second-Line Advanced RCC

The median duration of treatment was 6.4 months (range 0.03 to 22.0) for patients who received INLYTA and 5.0 months (range 0.03 to 20.1) for patients who received sorafenib. Dose modifications or temporary delay of treatment due to an adverse reaction occurred in 199/359 patients (55%) receiving INLYTA and 220/355 patients (62%) receiving sorafenib. Permanent discontinuation due to an adverse reaction occurred in 34/359 patients (9%) receiving INLYTA and 46/355 patients (13%) receiving sorafenib.

The most common (≥20%) adverse reactions observed following treatment with INLYTA were diarrhea, hypertension, fatigue, decreased appetite, nausea, dysphonia, palmar-plantar erythrodysesthesia (hand-foot) syndrome, weight decreased, vomiting, asthenia, and constipation. Table 8 presents adverse reactions reported in ≥10% patients who received INLYTA or sorafenib.

Table 8: Adverse Reactions Occurring in ≥10% of Patients Who Received INLYTA or Sorafenib
Adverse Reaction [Percentages are treatment-emergent, all-causality events] | INLYTA |  | Sorafenib
Adverse Reaction [Percentages are treatment-emergent, all-causality events] | (N=359) |  | (N=355)
Adverse Reaction [Percentages are treatment-emergent, all-causality events] | All Grades [National Cancer Institute Common Terminology Criteria for Adverse Events, Version 3.0] | Grade 3/4 | All Grades | Grade 3/4
Adverse Reaction [Percentages are treatment-emergent, all-causality events] | % | % | % | %
Diarrhea | 55 | 11 | 53 | 7
Hypertension | 40 | 16 | 29 | 11
Fatigue | 39 | 11 | 32 | 5
Decreased appetite | 34 | 5 | 29 | 4
Nausea | 32 | 3 | 22 | 1
Dysphonia | 31 | 0 | 14 | 0
Palmar-plantar erythrodysesthesia syndrome | 27 | 5 | 51 | 16
Weight decreased | 25 | 2 | 21 | 1
Vomiting | 24 | 3 | 17 | 1
Asthenia | 21 | 5 | 14 | 3
Constipation | 20 | 1 | 20 | 1
Hypothyroidism | 19 | <1 | 8 | 0
Cough | 15 | 1 | 17 | 1
Mucosal inflammation | 15 | 1 | 12 | 1
Arthralgia | 15 | 2 | 11 | 1
Stomatitis | 15 | 1 | 12 | <1
Dyspnea | 15 | 3 | 12 | 3
Abdominal pain | 14 | 2 | 11 | 1
Headache | 14 | 1 | 11 | 0
Pain in extremity | 13 | 1 | 14 | 1
Rash | 13 | <1 | 32 | 4
Proteinuria | 11 | 3 | 7 | 2
Dysgeusia | 11 | 0 | 8 | 0
Dry skin | 10 | 0 | 11 | 0
Dyspepsia | 10 | 0 | 2 | 0
Pruritus | 7 | 0 | 12 | 0
Alopecia | 4 | 0 | 32 | 0
Erythema | 2 | 0 | 10 | <1

Selected adverse reactions (all grades) that were reported in <10% of patients treated with INLYTA included dizziness (9%), upper abdominal pain (8%), myalgia (7%), dehydration (6%), epistaxis (6%), anemia (4%), hemorrhoids (4%), hematuria (3%), tinnitus (3%), lipase increased (3%), glossodynia (3%), pulmonary embolism (2%), rectal hemorrhage (2%), hemoptysis (2%), deep vein thrombosis (1%), retinal-vein occlusion/thrombosis (1%), polycythemia (1%), and transient ischemic attack (1%).

Table 9 presents the most common laboratory abnormalities reported in ≥10% patients who received INLYTA or sorafenib.

Table 9: Laboratory Abnormalities Occurring in ≥10% of Patients Who Received INLYTA or Sorafenib
Laboratory Abnormality | N | INLYTA |  | N | Sorafenib
Laboratory Abnormality | N | All Grades [National Cancer Institute Common Terminology Criteria for Adverse Events, Version 3.0] | Grade 3/4 | N | All Grades | Grade 3/4
Laboratory Abnormality | N | % | % | N | % | %
Hematology
Hemoglobin decreased | 320 | 35 | <1 | 316 | 52 | 4
Lymphocytes (absolute) decreased | 317 | 33 | 3 | 309 | 36 | 4
Platelets decreased | 312 | 15 | <1 | 310 | 14 | 0
White blood cells decreased | 320 | 11 | 0 | 315 | 16 | <1
Chemistry
Creatinine increased | 336 | 55 | 0 | 318 | 41 | <1
Bicarbonate decreased | 314 | 44 | <1 | 291 | 43 | 0
Hypocalcemia | 336 | 39 | 1 | 319 | 59 | 2
ALP increased | 336 | 30 | 1 | 319 | 34 | 1
Hyperglycemia | 336 | 28 | 2 | 319 | 23 | 2
Lipase increased | 338 | 27 | 5 | 319 | 46 | 15
Amylase increased | 338 | 25 | 2 | 319 | 33 | 2
ALT increased | 331 | 22 | <1 | 313 | 22 | 2
AST increased | 331 | 20 | <1 | 311 | 25 | 1
Hypernatremia | 338 | 17 | 1 | 319 | 13 | 1
Hypoalbuminemia | 337 | 15 | <1 | 319 | 18 | 1
Hyperkalemia | 333 | 15 | 3 | 314 | 10 | 3
Hypoglycemia | 336 | 11 | <1 | 319 | 8 | <1
Hyponatremia | 338 | 13 | 4 | 319 | 11 | 2
Hypophosphatemia | 336 | 13 | 2 | 318 | 49 | 16
ALP: alkaline phosphatase; ALT: alanine aminotransferase; AST: aspartate aminotransferase

Selected laboratory abnormalities (all grades) that were reported in <10% of patients treated with INLYTA included hemoglobin increased (above the upper limit of normal) (9% for INLYTA versus 1% for sorafenib) and hypercalcemia (6% for INLYTA versus 2% for sorafenib).

6.2 Postmarketing Experience

The following adverse reactions have been identified during postapproval use of INLYTA. Because these reactions are reported voluntarily from a population of uncertain size, it is not always possible to reliably estimate their frequency or establish a causal relationship to drug exposure.

Vascular disorders: arterial (including aortic), aneurysms, dissections, and rupture.

7 DRUG INTERACTIONS

7.1 CYP3A4/5 Inhibitors

Co-administration of ketoconazole, a strong inhibitor of CYP3A4/5, increased the plasma exposure of axitinib in healthy volunteers. Co-administration of INLYTA with strong CYP3A4/5 inhibitors should be avoided. Grapefruit or grapefruit juice may also increase axitinib plasma concentrations and should be avoided. Selection of concomitant medication with no or minimal CYP3A4/5 inhibition potential is recommended. If a strong CYP3A4/5 inhibitor must be co-administered, the INLYTA dose should be reduced [see Dosage and Administration (2.2) and Clinical Pharmacology (12.3)].

7.2 CYP3A4/5 Inducers

Co-administration of rifampin, a strong inducer of CYP3A4/5, reduced the plasma exposure of axitinib in healthy volunteers. Co-administration of INLYTA with strong CYP3A4/5 inducers (e.g., rifampin, dexamethasone, phenytoin, carbamazepine, rifabutin, rifapentine, phenobarbital, and St. John's wort) should be avoided. Selection of concomitant medication with no or minimal CYP3A4/5 induction potential is recommended [see Dosage and Administration (2.2), Clinical Pharmacology (12.3)]. Moderate CYP3A4/5 inducers (e.g., bosentan, efavirenz, etravirine, modafinil, and nafcillin) may also reduce the plasma exposure of axitinib and should be avoided if possible.

8 USE IN SPECIFIC POPULATIONS

8.1 Pregnancy

Risk Summary

Based on findings in animal studies and its mechanism of action, INLYTA can cause fetal harm when administered to a pregnant woman. There are no available human data to inform the drug-associated risk. In developmental toxicity studies, axitinib was teratogenic, embryotoxic and fetotoxic in mice at exposures lower than human exposures at the recommended starting dose (see Data). Advise females of reproductive potential of the potential risk to a fetus.

The background risk of major birth defects and miscarriage for the indicated populations are unknown. However, the background risk in the United States (U.S.) general population of major birth defects is 2%–4% and of miscarriage is 15%–20% of clinically recognized pregnancies.

When INLYTA is used in combination with avelumab or pembrolizumab, refer to the full prescribing information of avelumab or pembrolizumab for pregnancy information.

Data

Animal Data

Oral axitinib administered twice daily to female mice prior to mating and through the first week of pregnancy caused an increase in post-implantation loss at all doses tested (≥15 mg/kg/dose, approximately 10 times the systemic exposure (AUC) in patients at the recommended starting dose). In an embryo-fetal developmental toxicity study, pregnant mice received oral doses of 0.15, 0.5 and 1.5 mg/kg/dose axitinib twice daily during the period of organogenesis. Embryo-fetal toxicities observed in the absence of maternal toxicity included malformation (cleft palate) at 1.5 mg/kg/dose (approximately 0.5 times the AUC in patients at the recommended starting dose) and variation in skeletal ossification at ≥0.5 mg/kg/dose (approximately 0.15 times the AUC in patients at the recommended starting dose).

8.2 Lactation

Risk Summary

There are no data on the presence of axitinib in human milk, or its effects on the breastfed child or on milk production. Because of the potential for serious adverse reactions in a breastfed child from INLYTA, advise lactating women not to breastfeed during treatment and for 2 weeks after the last dose.

When INLYTA is used in combination with avelumab or pembrolizumab, refer to the full prescribing information of avelumab or pembrolizumab for lactation information.

8.3 Females and Males of Reproductive Potential

Based on findings in animal studies, INLYTA can cause fetal harm when administered to a pregnant woman [see Use in Specific Populations (8.1)]. When INLYTA is used in combination with avelumab or pembrolizumab, refer to the full prescribing information of avelumab or pembrolizumab for contraception information.

Pregnancy Testing

Verify pregnancy status in females of reproductive potential prior to initiating treatment with INLYTA.

Contraception

Females

Advise females of reproductive potential to use effective contraception during treatment with INLYTA and for 1 week after the last dose.

Males

Based on findings in animal studies, advise males with female partners of reproductive potential to use effective contraception during treatment and for 1 week after the last dose.

Infertility

Females and Males

Based on findings in animals, INLYTA may impair fertility in females and males of reproductive potential [see Nonclinical Toxicology (13.1)].

8.4 Pediatric Use

The safety and effectiveness of INLYTA in pediatric patients have not been established.

The safety and effectiveness of INLYTA were assessed, but not established, in two open label studies: a dose finding study of INLYTA as a single agent in 17 pediatric patients aged 5 to <17 years with recurrent or refractory solid tumors (ADVL1315, NCT02164838) and a randomized study of INLYTA as a single agent or in combination in 7 pediatric patients aged 7 to <17 years (AREN1721, NCT03595124).

No new safety signals were observed with INLYTA in pediatric patients across these studies.

Exposure in pediatric patients who received INLYTA at the maximum tolerated dosage were lower than those previously observed in adults who received the approved recommended starting dosage.

Juvenile Animal Toxicity Data

Toxicities in bone and teeth were observed in immature mice and dogs administered oral axitinib twice daily for 1 month or longer. Effects in bone consisted of thickened growth plates in mice and dogs at ≥15 mg/kg/dose (approximately 6 and 15 times, respectively, the systemic exposure (AUC) in patients at the recommended starting dose). Abnormalities in growing incisor teeth (including dental caries, malocclusions and broken and/or missing teeth) were observed in mice administered oral axitinib twice daily at ≥5 mg/kg/dose (approximately 1.5 times the AUC in patients at the recommended starting dose). Other toxicities of potential concern to pediatric patients have not been evaluated in juvenile animals.

8.5 Geriatric Use

In a controlled clinical study with INLYTA for the treatment of patients with RCC, 123/359 patients (34%) treated with INLYTA were ≥65 years of age. Although greater sensitivity in some older individuals cannot be ruled out, no overall differences were observed in the safety and effectiveness of INLYTA between patients who were ≥65 years of age and younger.

Of the 434 patients randomized to INLYTA 5 mg twice daily administered in combination with avelumab 10 mg/kg in the JAVELIN Renal 101 trial, 38% were 65 years or older and 8% were 75 years or older. No overall difference in safety or efficacy was reported between patients who were ≥65 years of age and younger.

Of the 432 patients randomized to INLYTA 5 mg twice daily administered in combination with pembrolizumab 200 mg in the KEYNOTE-426 trial, 40% were 65 years or older. No overall difference in safety or efficacy was reported between patients who were ≥65 years of age and younger.

No dosage adjustment is required in elderly patients [see Dosage and Administration (2.2), Clinical Pharmacology (12.3)].

8.6 Hepatic Impairment

In a dedicated hepatic impairment trial, compared to subjects with normal hepatic function, systemic exposure following a single dose of INLYTA was similar in subjects with baseline mild hepatic impairment (Child-Pugh class A) and higher in subjects with baseline moderate hepatic impairment (Child-Pugh class B).

No starting dose adjustment is required when administering INLYTA to patients with mild hepatic impairment (Child-Pugh class A). A starting dose decrease is recommended when administering INLYTA to patients with moderate hepatic impairment (Child-Pugh class B) [see Dosage and Administration (2.2), Warnings and Precautions (5.12), Clinical Pharmacology (12.3)].

INLYTA has not been studied in subjects with severe hepatic impairment (Child-Pugh class C).

8.7 Renal Impairment

No dedicated renal impairment trial for axitinib has been conducted. Based on the population pharmacokinetic analyses, no significant difference in axitinib clearance was observed in patients with pre-existing mild to severe renal impairment (15 mL/min ≤creatinine clearance [CLcr] <89 mL/min) [see Clinical Pharmacology (12.3)]. No starting dose adjustment is needed for patients with pre-existing mild to severe renal impairment. Caution should be used in patients with end-stage renal disease (CLcr <15 mL/min).

10 OVERDOSAGE

There is no specific treatment for INLYTA overdose.

In a controlled clinical study with INLYTA for the treatment of patients with RCC, 1 patient inadvertently received a dose of 20 mg twice daily for 4 days and experienced dizziness (Grade 1).

In a clinical dose finding study with INLYTA, subjects who received starting doses of 10 mg twice daily or 20 mg twice daily experienced adverse reactions which included hypertension, seizures associated with hypertension, and fatal hemoptysis.

In cases of suspected overdose, INLYTA should be withheld and supportive care instituted.

11 DESCRIPTION

INLYTA (axitinib) is a kinase inhibitor. Axitinib has the chemical name N-methyl-2-[3-((E)-2-pyridin-2-yl-vinyl)-1H-indazol-6-ylsulfanyl]-benzamide. The molecular formula is C22H18N4OS and the molecular weight is 386.47 Daltons. The chemical structure is:

Axitinib is a white to light-yellow powder with a pKa of 4.8. The solubility of axitinib in aqueous media over the range pH 1.1 to pH 7.8 is in excess of 0.2 µg/mL. The partition coefficient (n-octanol/water) is 3.5.

INLYTA is supplied as red, film-coated tablets containing either 1 mg or 5 mg of axitinib together with microcrystalline cellulose, lactose monohydrate, croscarmellose sodium, magnesium stearate, and Opadry® II red 32K15441 as inactive ingredients. The Opadry II red 32K15441 film coating contains lactose monohydrate, HPMC 2910/Hypromellose 15cP, titanium dioxide, triacetin (glycerol triacetate), and red iron oxide.

12 CLINICAL PHARMACOLOGY

12.1 Mechanism of Action

Axitinib has been shown to inhibit receptor tyrosine kinases including vascular endothelial growth factor receptors (VEGFR)-1, VEGFR-2, and VEGFR-3 at therapeutic plasma concentrations. These receptors are implicated in pathologic angiogenesis, tumor growth, and cancer progression. VEGF-mediated endothelial cell proliferation and survival were inhibited by axitinib in vitro and in mouse models. Axitinib was shown to inhibit tumor growth and phosphorylation of VEGFR-2 in tumor xenograft mouse models.

12.2 Pharmacodynamics

The effect of a single oral dose of INLYTA (5 mg) in the absence and presence of 400 mg ketoconazole on the QTc interval was evaluated in a randomized, single-blinded, two-way crossover study in 35 healthy subjects. No large changes in mean QTc interval (i.e., >20 ms) from placebo were detected up to 3 hours post-dose. However, small increases in mean QTc interval (i.e., <10 ms) cannot be ruled out.

12.3 Pharmacokinetics

The population pharmacokinetic analysis pooled data from 17 trials in healthy subjects and patients with cancer. A two-compartment disposition model with first-order absorption and lag-time adequately describes the axitinib concentration-time profile.

Absorption and Distribution

Following single oral 5-mg dose administration, the median Tmax ranged from 2.5 to 4.1 hours. Based on the plasma half-life, steady state is expected within 2 to 3 days of dosing. Dosing of axitinib at 5 mg twice daily resulted in approximately 1.4-fold accumulation compared to administration of a single dose. At steady state, axitinib exhibits approximately linear pharmacokinetics within the 1-mg to 20-mg dose range. The mean absolute bioavailability of axitinib after an oral 5 mg dose is 58%.

Compared to overnight fasting, administration of INLYTA with a moderate fat meal resulted in 10% lower AUC and a high fat, high-calorie meal resulted in 19% higher AUC. INLYTA can be administered with or without food [see Dosage and Administration (2.1)].

Axitinib is highly bound (>99%) to human plasma proteins with preferential binding to albumin and moderate binding to α1-acid glycoprotein. In patients with advanced RCC (n=20), at the 5 mg twice daily dose in the fed state, the geometric mean (CV%) Cmax and AUC0–24 were 27.8 (79%) ng/mL and 265 (77%) ng.h/mL, respectively. The geometric mean (CV%) clearance and apparent volume of distribution were 38 (80%) L/h and 160 (105%) L, respectively.

Metabolism and Elimination

The plasma half-life of INLYTA ranges from 2.5 to 6.1 hours. Axitinib is metabolized primarily in the liver by CYP3A4/5 and to a lesser extent by CYP1A2, CYP2C19, and UGT1A1. Following oral administration of a 5-mg radioactive dose of axitinib, approximately 41% of the radioactivity was recovered in feces and approximately 23% was recovered in urine. Unchanged axitinib, accounting for 12% of the dose, was the major component identified in feces. Unchanged axitinib was not detected in urine; the carboxylic acid and sulfoxide metabolites accounted for the majority of radioactivity in urine. In plasma, the N-glucuronide metabolite represented the predominant radioactive component (50% of circulating radioactivity) and unchanged axitinib and the sulfoxide metabolite each accounted for approximately 20% of the circulating radioactivity.

The sulfoxide and N-glucuronide metabolites show approximately ≥400-fold less in vitro potency against VEGFR-2 compared to axitinib.

Drug-Drug Interactions

Effects of Other Drugs on INLYTA

Axitinib is metabolized primarily in the liver by CYP3A4/5. Additionally, the aqueous solubility of axitinib is pH dependent, with higher pH resulting in lower solubility. The effects of a strong CYP3A4/5 inhibitor, a strong CYP3A4/5 inducer, and an antacid on the pharmacokinetics of axitinib are presented in Figure 1 [see Dosage and Administration (2.2) and Drug Interactions (7.1, 7.2)].

Figure 1. Impact of Co-administered Drugs and Hepatic Impairment on Axitinib Pharmacokinetics

Effects of INLYTA on Other Drugs

In vitro studies demonstrated that axitinib has the potential to inhibit CYP1A2 and CYP2C8. However, co-administration of axitinib with paclitaxel, a CYP2C8 substrate, did not increase plasma concentrations of paclitaxel in patients.

In vitro studies indicated that axitinib does not inhibit CYP2A6, CYP2C9, CYP2C19, CYP2D6, CYP2E1, CYP3A4/5, or UGT1A1 at therapeutic plasma concentrations. In vitro studies in human hepatocytes indicated that axitinib does not induce CYP1A1, CYP1A2, or CYP3A4/5.

Axitinib is an inhibitor of the efflux transporter P-glycoprotein (P-gp) in vitro. However, INLYTA is not expected to inhibit P-gp at therapeutic plasma concentrations.

Specific Populations

Patients with Hepatic Impairment

The effects of hepatic impairment on the pharmacokinetics of axitinib are presented in Figure 1 [see Dosage and Administration (2.2), Warnings and Precautions (5.12), Use in Specific Populations (8.6)].

Patients with Renal Impairment

Population pharmacokinetic analysis (based on pre-existing renal function) was carried out in 590 healthy volunteers and patients, including five with severe renal impairment (15 mL/min ≤CLcr <29 mL/min), 64 with moderate renal impairment (30 mL/min ≤CLcr <59 mL/min), and 139 with mild renal impairment (60 mL/min ≤CLcr <89 mL/min). Mild to severe renal impairment did not have meaningful effects on the pharmacokinetics of axitinib. Data from only one patient with end-stage renal disease are available [see Use in Specific Populations (8.7)].

Other Intrinsic Factors

Population pharmacokinetic analyses indicate that there are no clinically relevant effects of age, gender, race, body weight, body surface area, UGT1A1 genotype, or CYP2C19 genotype on the clearance of axitinib.

INLYTA in Combination with Avelumab

When INLYTA 5 mg was administered in combination with avelumab 10 mg/kg, the respective exposures of INLYTA and avelumab were comparable to the single agents. There was no evidence to suggest a clinically relevant change of avelumab clearance over time in patients with advanced RCC.

INLYTA in Combination with Pembrolizumab

When INLYTA 5 mg was administered in combination with pembrolizumab 200 mg, the respective exposures of INLYTA and pembrolizumab were comparable to the single agents.

13 NONCLINICAL TOXICOLOGY

13.1 Carcinogenesis, Mutagenesis, Impairment of Fertility

Carcinogenicity studies have not been conducted with axitinib.

Axitinib was not mutagenic in an in vitro bacterial reverse mutation (Ames) assay and was not clastogenic in the in vitro human lymphocyte chromosome aberration assay. Axitinib was genotoxic in the in vivo mouse bone marrow micronucleus assay.

INLYTA has the potential to impair reproductive function and fertility in humans. In repeat-dose toxicology studies, findings in the male reproductive tract were observed in the testes/epididymis (decreased organ weight, atrophy or degeneration, decreased numbers of germinal cells, hypospermia or abnormal sperm forms, reduced sperm density and count) at ≥15 mg/kg/dose administered orally twice daily in mice (approximately 7 times the systemic exposure (AUC) in patients at the recommended starting dose) and ≥1.5 mg/kg/dose administered orally twice daily in dogs (approximately 0.1 times the AUC in patients at the recommended starting dose). Findings in the female reproductive tract in mice and dogs included signs of delayed sexual maturity, reduced or absent corpora lutea, decreased uterine weights and uterine atrophy at ≥5 mg/kg/dose (approximately 1.5 or 0.3 times the AUC in patients at the recommended starting dose compared to mice and dogs, respectively).

In a fertility study in mice, axitinib did not affect mating or fertility rate when administered orally twice daily to males at any dose tested up to 50 mg/kg/dose following at least 70 days of administration (approximately 57 times the AUC in patients at the recommended starting dose). In female mice, reduced fertility and embryonic viability were observed at all doses tested (≥15 mg/kg/dose administered orally twice daily) following at least 15 days of treatment with axitinib (approximately 10 times the AUC in patients at the recommended starting dose).

14 CLINICAL STUDIES

14.1 First-Line Advanced RCC

INLYTA in Combination with Avelumab

The efficacy and safety of INLYTA in combination with avelumab was demonstrated in the JAVELIN Renal 101 trial (NCT02684006), a randomized, multicenter, open-label, study of INLYTA in combination with avelumab in 886 patients with untreated advanced RCC regardless of tumor PD-L1 expression [intent-to-treat (ITT) population]. Patients with autoimmune disease or conditions requiring systemic immunosuppression were excluded.

Randomization was stratified according to Eastern Cooperative Oncology Group (ECOG) Performance Status (PS) (0 vs. 1) and region (United States vs. Canada/Western Europe vs. the rest of the world). Patients were randomized (1:1) to one of the following treatment arms:

- INLYTA 5 mg twice daily orally was given in combination with avelumab 10 mg/kg intravenous infusion every 2 weeks (N=442). Patients who tolerated INLYTA 5 mg twice daily without Grade 2 or greater INLYTA-related adverse events for 2 consecutive weeks could increase to 7 mg and then subsequently to 10 mg twice daily. INLYTA could be interrupted or reduced to 3 mg twice daily and subsequently to 2 mg twice daily to manage toxicity.
- Sunitinib 50 mg once daily orally for 4 weeks followed by 2 weeks off (N=444) until radiographic or clinical progression or unacceptable toxicity.

Treatment with INLYTA and avelumab continued until RECIST v1.1-defined progression of disease by Blinded Independent Central Review (BICR) assessment or unacceptable toxicity. Administration of INLYTA and avelumab was permitted beyond RECIST-defined disease progression if the patient was clinically stable and considered to be deriving clinical benefit by the investigator. Assessment of tumor status was performed at baseline, after randomization at 6 weeks, then every 6 weeks thereafter up to 18 months after randomization, and every 12 weeks thereafter until documented confirmed disease progression by BICR.

Baseline characteristics were a median age of 61 years (range: 27 to 88), 38% of patients were 65 years or older, 75% were male, 75% were White, and the ECOG PS was 0 (63%) or 1 (37%), respectively. Patient distribution by International Metastatic Renal Cell Carcinoma Database (IMDC) risk groups was 21% favorable, 62% intermediate, and 16% poor.

The major efficacy outcome measures were progression-free survival (PFS), as assessed by an BICR using RECIST v1.1 and overall survival (OS) in patients with PD-L1-positive tumors using a clinical trial assay (PD-L1 expression level ≥1%). Since PFS was statistically significant in patients with PD-L1-positive tumors [HR 0.61 (95% CI: 0.48, 0.79)], it was then tested in the ITT population and a statistically significant improvement in PFS in the ITT population was also demonstrated.

With a median overall survival follow-up of 19 months, overall survival data were immature with 27% deaths in the ITT population.

Efficacy results are presented in Table 10 and Figure 2.

Table 10: Efficacy Results from JAVELIN Renal 101 Trial-ITT
Efficacy Endpoints (Based on BICR Assessment) | INLYTA plus avelumab (N=422) | Sunitinib (N=444)
Progression-Free Survival (PFS)
Events (%) | 180 (41) | 216 (49)
Median in Months (95% CI) | 13.8 (11.1, NE) | 8.4 (6.9, 11.1)
Hazard ratio (95% CI) | 0.69 (0.56, 0.84)
2-sided p-value [p-value based on stratified log-rank.] | 0.0002
Confirmed Objective Response Rate (ORR)
Objective Response Rate n (%) | 227 (51.4) | 114 (25.7)
(95% CI) | (46.6, 56.1) | (21.7, 30.0)
Complete Response (CR) n (%) | 15 (3.4) | 8 (1.8)
Partial Response (PR) n (%) | 212 (48) | 106 (24)
BICR: Blinded Independent Central Review; CI: Confidence interval; NE: Not estimable.

Figure 2. K-M Estimates for PFS Based on BICR Assessment - ITT

INLYTA in Combination with Pembrolizumab

The efficacy of INLYTA in combination with pembrolizumab was investigated in KEYNOTE-426 (NCT02853331), a randomized, multicenter, open-label trial conducted in 861 patients who had not received systemic therapy for advanced RCC. Patients were enrolled regardless of PD-L1 tumor expression status. Patients with active autoimmune disease requiring systemic immunosuppression within the last 2 years were ineligible. Randomization was stratified by International Metastatic RCC Database Consortium (IMDC) risk categories (favorable versus intermediate versus poor) and geographic region (North America versus Western Europe versus "Rest of the World").

Patients were randomized (1:1) to one of the following treatment arms:

- INLYTA 5 mg orally, twice daily in combination with pembrolizumab 200 mg intravenously every 3 weeks up to 24 months. Patients who tolerated INLYTA 5 mg twice daily for 2 consecutive cycles (6 weeks) could increase to 7 mg and then subsequently to 10 mg twice daily. INLYTA could be interrupted or reduced to 3 mg twice daily and subsequently to 2 mg twice daily to manage toxicity.
- Sunitinib 50 mg orally, once daily for 4 weeks and then off treatment for 2 weeks.

Treatment with INLYTA and pembrolizumab continued until RECIST v1.1-defined progression of disease or unacceptable toxicity. Administration of INLYTA and pembrolizumab was permitted beyond RECIST-defined disease progression if the patient was clinically stable and considered to be deriving clinical benefit by the investigator. Assessment of tumor status was performed at baseline, after randomization at Week 12, then every 6 weeks thereafter until Week 54, and then every 12 weeks thereafter.

The study population characteristics were: median age of 62 years (range: 26 to 90); 38% age 65 or older; 73% male; 79% White and 16% Asian; 20% and 80% of patients had a baseline KPS of 70 to 80 and 90 to 100, respectively; and patient distribution by IMDC risk categories was 31% favorable, 56% intermediate and 13% poor.

The main efficacy outcome measures were OS and PFS as assessed by BICR according to RECIST v1.1, modified to follow a maximum of 10 target lesions and a maximum of 5 target lesions per organ. Additional efficacy outcome measures included ORR, as assessed by BICR. A statistically significant improvement in OS was demonstrated at the first pre-specified interim analysis in patients randomized to INLYTA in combination with pembrolizumab compared with sunitinib. The trial also demonstrated statistically significant improvements in PFS and ORR.

An updated OS analysis was conducted when 418 deaths were observed based on the planned number of deaths for the pre-specified final analysis. Table 11 and Figure 3 summarize the efficacy results for KEYNOTE-426.

Table 11: Efficacy Results in KEYNOTE-426
Endpoint | INLYTA and Pembrolizumab N=432 | Sunitinib N=429
OS
Number of patients with event (%) | 59 (14%) | 97 (23%)
Median in months (95% CI) | NR (NR, NR) | NR (NR, NR)
Hazard ratio [Based on the stratified Cox proportional hazard model] (95% CI) | 0.53 (0.38, 0.74)
p-Value [Based on stratified log-rank test] | <0.0001 [p-Value (one-sided) is compared with the allocated alpha of 0.0001 for this interim analysis (with 39% of the planned number of events for final analysis).]
12-month OS rate | 90% (86, 92) | 78% (74, 82)
Updated OS
Number of patients with event (%) | 193 (45%) | 225 (52%)
Median in months (95% CI) | 45.7 (43.6, NR) | 40.1 (34.3, 44.2)
Hazard ratio (95% CI) | 0.73 (0.60, 0.88)
PFS
Number of patients with event (%) | 183 (42%) | 213 (50%)
Median in months (95% CI) | 15.1 (12.6, 17.7) | 11.0 (8.7, 12.5)
Hazard ratio (95% CI) | 0.69 (0.56, 0.84)
p-Value | 0.0001 [p-Value (one-sided) is compared with the allocated alpha of 0.0013 for this interim analysis (with 81% of the planned number of events for final analysis).]
ORR
Overall confirmed response rate (95% CI) | 59% (54, 64) | 36% (31, 40)
Complete response rate | 6% | 2%
Partial response rate | 53% | 34%
p-Value [Based on Miettinen and Nurminen method stratified by IMDC risk group and geographic region] | <0.0001
CI: confidence interval; NR: not reached; ORR: objective response rate; OS: overall survival; PFS: progression-free survival.

Figure 3. Kaplan-Meier Curve for Overall Survival in KEYNOTE-426

In an exploratory analysis, the updated analysis of OS in patients with IMDC favorable, intermediate, intermediate/poor, and poor risk demonstrated a HR of 1.17 (95% CI: 0.76, 1.80), 0.67 (95% CI: 0.52, 0.86), 0.64 (95% CI: 0.52, 0.80), and 0.51 (95% CI: 0.32, 0.81), respectively.

14.2 Second-Line Advanced RCC

The safety and efficacy of INLYTA were evaluated in a randomized, open-label, multicenter Phase 3 study. Patients (N=723) with advanced RCC whose disease had progressed on or after treatment with 1 prior systemic therapy, including sunitinib-, bevacizumab-, temsirolimus-, or cytokine-containing regimens were randomized (1:1) to receive INLYTA (N=361) or sorafenib (N=362). Progression-free survival (PFS) was assessed by a blinded independent central review committee. Other endpoints included objective response rate (ORR) and overall survival (OS).

Of the patients enrolled in this study, 389 patients (54%) had received 1 prior sunitinib-based therapy, 251 patients (35%) had received 1 prior cytokine-based therapy (interleukin-2 or interferon-alfa), 59 patients (8%) had received 1 prior bevacizumab-based therapy, and 24 patients (3%) had received 1 prior temsirolimus-based therapy. The baseline demographic and disease characteristics were similar between the INLYTA and sorafenib groups with regard to age (median 61 years), gender (72% male), race (75% white, 21% Asian), Eastern Cooperative Oncology Group (ECOG) performance status (55% 0, 45% 1), and histology (99% clear cell).

There was a statistically significant advantage for INLYTA over sorafenib for the endpoint of PFS (see Table 12 and Figure 4). There was no statistically significant difference between the arms in OS.

Table 12: Efficacy Results
Endpoint/Study Population | INLYTA | Sorafenib | HR (95% CI) | P-value
Overall ITT | N= 361 | N = 362
Median PFS [Time from randomization to progression or death due to any cause, whichever occurs first.] , [Assessed by independent radiology review according to RECIST.] in months (95% CI) | 6.7 (6.3, 8.6) | 4.7 (4.6, 5.6) | 0.67 (0.54, 0.81) | <0.0001 [One-sided p-value from a log-rank test of treatment stratified by ECOG performance status and prior therapy (comparison is considered statistically significant if the one-sided p-value is <0.023).]
Median OS in months (95% CI) | 20.1 (16.7, 23.4) | 19.2 (17.5, 22.3) | 0.97 (0.80, 1.17) | NS
ORR % (95% CI) | 19.4 (15.4, 23.9) | 9.4 (6.6, 12.9) | 2.06 [Risk ratio is used for ORR. A risk ratio >1 indicated a higher likelihood of responding in the axitinib arm; a risk ratio <1 indicated a higher likelihood of responding in the sorafenib arm.] (1.41, 3.00) | - [P-value not included since it was not adjusted for multiple testing.]
PFS by prior treatment
Sunitinib-refractory subgroup | N=194 | N=195
Median, months (95% CI) | 4.8 (4.5, 6.4) | 3.4 (2.8, 4.7) | 0.74 (0.57, 0.96) | -
Cytokine-refractory subgroup | N=126 | N=125
Median, months (95% CI) | 12.1 (10.1, 13.9) | 6.5 (6.3, 8.3) | 0.46 (0.32, 0.68) | -
CI: Confidence interval; HR: Hazard ratio (INLYTA/sorafenib); ITT: Intent-to-treat; ORR: Objective response rate; NS: Not significant; OS: Overall survival; PFS: Progression-free survival

Figure 4. Kaplan-Meier Curve for Progression-Free Survival by Independent Assessment (Intent-to-Treat Population)

16 HOW SUPPLIED/STORAGE AND HANDLING

INLYTA tablets are supplied as follows:

- 1 mg tablets are red film-coated, oval tablets debossed with "Pfizer" on one side and "1 XNB" on the other; available in bottles of 180: NDC 0069-0145-01.
- 5 mg tablets are red film-coated, triangular tablets debossed with "Pfizer" on one side and "5 XNB" on the other; available in bottles of 60: NDC 0069-0151-11.
- Store at 20°C to 25°C (68°F to 77°F); excursions permitted to 15°C to 30°C (59°F to 86°F) [see USP Controlled Room Temperature].

17 PATIENT COUNSELING INFORMATION

Advise the patient to read the FDA-approved patient labeling (Patient Information).

Hypertension

Advise patients that hypertension may develop during INLYTA treatment and that blood pressure should be monitored regularly during treatment [see Warnings and Precautions (5.1)].

Arterial/Venous Thromboembolic Events

Advise patients that arterial and venous thromboembolic events have been observed during INLYTA treatment and to inform their doctor if they experience symptoms suggestive of thromboembolic events [see Warnings and Precautions (5.2, 5.3)].

Hemorrhage

Advise patients that INLYTA may increase the risk of bleeding and to promptly inform their doctor of any bleeding episodes [see Warnings and Precautions (5.4)].

Cardiac Failure

Advise patients that cardiac failure may develop during INLYTA treatment and that signs or symptoms of cardiac failure should be regularly monitored for during treatment [see Warnings and Precautions (5.5)].

Gastrointestinal Disorders

Advise patients that gastrointestinal disorders such as diarrhea, nausea, vomiting, and constipation may develop during INLYTA treatment and to seek immediate medical attention if they experience persistent or severe abdominal pain because cases of gastrointestinal perforation and fistula have been reported in patients taking INLYTA [see Warnings and Precautions (5.6) and Adverse Reactions (6.1)].

Abnormal Thyroid Function

Advise patients that abnormal thyroid function may develop during INLYTA treatment and to inform their doctor if symptoms of abnormal thyroid function occur [see Warnings and Precautions (5.7)].

Impaired Wound Healing

Advise patients that INLYTA may impair wound healing. Advise patients to inform their healthcare provider of any planned surgical procedure [see Warnings and Precautions (5.8)].

Reversible Posterior Leukoencephalopathy Syndrome

Advise patients to inform their doctor if they have worsening of neurological function consistent with RPLS (headache, seizure, lethargy, confusion, blindness and other visual and neurologic disturbances) [see Warnings and Precautions (5.9)].

Hepatotoxicity

Inform patients of the signs and symptoms of hepatotoxicity. Advise patients to contact their healthcare provider immediately for signs or symptoms of hepatotoxicity [see Warnings and Precautions (5.11)].

Major Adverse Cardiovascular Events

Advise patients receiving INLYTA in combination with avelumab to contact their healthcare provider immediately for signs or symptoms of cardiovascular events including but not limited to new or worsening chest discomfort, dyspnea, or peripheral edema [see Warnings and Precautions (5.13)].

Embryo-Fetal Toxicity

Advise females to inform their healthcare provider if they are pregnant or become pregnant. Inform female patients of the risk to a fetus and potential loss of the pregnancy [see Use in Specific Populations (8.1)].

Advise females of reproductive potential to use effective contraception during treatment with INLYTA and for 1 week after the last dose.

Advise male patients with female partners of reproductive potential to use effective contraception during treatment and for 1 week following the last dose [see Warnings and Precautions (5.14) and Use in Specific Populations (8.3)].

When INLYTA is used in combination with avelumab or pembrolizumab, refer to the full prescribing information of avelumab or pembrolizumab for pregnancy and contraception information.

Lactation

Advise patients not to breastfeed while taking INLYTA and for 2 weeks after receiving the last dose [see Use in Specific Populations (8.2)].

When INLYTA is used in combination with avelumab or pembrolizumab, refer to the full prescribing information of avelumab or pembrolizumab for lactation information.

Infertility

Advise males and females of reproductive potential that INLYTA may impair fertility [see Use in Specific Populations (8.3)].

Concomitant Medications

Advise patients to inform their doctor of all concomitant medications, vitamins, or dietary and herbal supplements.

This product's labeling may have been updated. For the most recent prescribing information, please visit www.pfizer.com.

LAB-0561-8.0

PATIENT INFORMATION
INLYTA® (in-ly-ta)
(axitinib)
tablets

Important information: If your healthcare provider prescribes INLYTA for you to be taken with avelumab or pembrolizumab, also read the Medication Guide for avelumab or pembrolizumab.

What is INLYTA?
INLYTA is a prescription medicine used to treat kidney cancer that has spread or cannot be removed by surgery (advanced renal cell carcinoma or RCC):

- in combination with avelumab or pembrolizumab as your first treatment.
- alone when 1 prior drug treatment regimen for your RCC has not worked.

It is not known if INLYTA is safe and effective in children.

Before taking INLYTA, tell your healthcare provider about all of your medical conditions, including if you:

- have high blood pressure
- have thyroid problems
- have liver problems
- have a history of blood clots in your veins or arteries (types of blood vessels), including stroke, heart attack, or change in vision
- have any bleeding problems
- have a history of heart problems, including heart failure
- have an unhealed wound
- plan to have surgery or have had a recent surgery. You should stop taking INLYTA for at least 2 days before planned surgery. See "What are the possible side effects of INLYTA?"

For females, tell your healthcare provider if you:

- are pregnant or plan to become pregnant. Taking INLYTA during pregnancy can harm your unborn baby. You should not become pregnant during treatment with INLYTA.
- are able to become pregnant. You should have a pregnancy test before you start treatment with INLYTA. Use effective birth control during treatment and for 1 week after your last dose of INLYTA. Talk to your healthcare provider about birth control methods that you can use to prevent pregnancy during this time.
- are breastfeeding or plan to breastfeed. It is not known if INLYTA passes into your breast milk. Do not breastfeed during treatment and for 2 weeks after your last dose of INLYTA.

For males with female partners who are able to become pregnant:

- Use effective birth control during treatment and for 1 week after your last dose of INLYTA.
- If your female partner becomes pregnant during your treatment with INLYTA, tell your healthcare provider right away.

Tell your healthcare provider about all the medicines you take, including prescription and over-the-counter medicines, vitamins, and herbal supplements. INLYTA and certain other medicines can affect each other causing serious side effects.
Talk with your healthcare provider before you start taking any new medicine. Know the medicines you take. Keep a list of them to show your healthcare provider and pharmacist when you get a new medicine.

How should I take INLYTA?

- Take INLYTA exactly as prescribed by your healthcare provider.
- Your healthcare provider may change your dose if needed.
- INLYTA can be taken with or without food.
- Take INLYTA 2 times a day about 12 hours apart.
- Swallow INLYTA tablets whole with a glass of water.
- Your healthcare provider should check your blood pressure regularly during treatment with INLYTA.
- If you vomit or miss a dose of INLYTA, take your next dose at your regular time. Do not take two doses at the same time.
- If you take too much INLYTA, call your healthcare provider or go to the nearest hospital emergency room right away.

What should I avoid while taking INLYTA?

- Do not drink grapefruit juice or eat grapefruit. Grapefruit may increase the amount of INLYTA in your blood.

What are the possible side effects of INLYTA?
INLYTA may cause serious side effects, including:

- High blood pressure (hypertension). High blood pressure is common with INLYTA and may sometimes be severe. Your healthcare provider should check your blood pressure regularly during treatment with INLYTA. If you develop blood pressure problems, your healthcare provider may prescribe medicine to treat your high blood pressure, lower your dose, or stop your treatment with INLYTA.
- Blood clots in your veins or arteries. INLYTA can cause blood clots which can be serious, and sometimes lead to death. Get emergency help and call your healthcare provider if you get any of the following symptoms:

- chest pain or pressure
- pain in your arms, back, neck or jaw
- shortness of breath

- numbness or weakness on one side of your body
- trouble talking
- headache
- vision changes

- Bleeding. INLYTA can cause bleeding which can be serious, and sometimes lead to death. Call your healthcare provider right away or get medical help if you develop any of the following signs or symptoms:

- unexpected bleeding or bleeding that lasts a long time, such as:

- unusual bleeding from the gums
- menstrual bleeding or vaginal bleeding that is heavier than normal
- bleeding that is severe or you cannot control
- pink or brown urine

- red or black stools (looks like tar)
- bruises that happen without a known cause or get larger
- cough up blood or blood clots
- vomit blood or your vomit looks like "coffee grounds"

- unexpected pain, swelling, or joint pain
- headaches, feeling dizzy or weak

- Heart failure. Your healthcare provider should check you for signs or symptoms of heart failure regularly during treatment with INLYTA. Heart failure can be serious and can sometimes lead to death. Tell your healthcare provider if you have any of the following symptoms during your treatment with INLYTA:

- tiredness
- swelling of your stomach-area (abdomen), legs or ankles

- shortness of breath
- protruding neck veins

- Tear in your stomach or intestinal wall (perforation). A tear in your stomach or intestinal wall can be serious and can sometimes lead to death. Get medical help right away if you get the following symptoms:
  - severe stomach-area (abdominal) pain or stomach-area pain that does not go away
  - vomit blood
  - red or black stools

- Thyroid gland problems. Your healthcare provider should do blood tests to check your thyroid gland function before and during your treatment with INLYTA. Tell your healthcare provider if you have any of the following symptoms during your treatment with INLYTA:

- tiredness that worsens or that does not go away
- feeling hot or cold
- your voice deepens

- weight gain or weight loss
- hair loss
- muscle cramps and aches

- Risk of wound healing problems. Wounds may not heal properly during INLYTA treatment. Tell your healthcare provider if you plan to have any surgery before starting or during treatment with INLYTA.
  - You should stop taking INLYTA at least 2 days before planned surgery.
  - Your healthcare provider should tell you when you may start taking INLYTA again after surgery.

- Reversible Posterior Leukoencephalopathy Syndrome (RPLS). A condition called reversible posterior leukoencephalopathy syndrome (RPLS) can happen during treatment with INLYTA. Call your healthcare provider right away if you get:

- headache
- seizures
- weakness

- confusion
- high blood pressure
- blindness or change in vision
- problems thinking

- Protein in your urine. Your healthcare provider should check your urine for protein before and during your treatment with INLYTA. If you develop protein in your urine, your healthcare provider may decrease your dose of INLYTA or stop your treatment.
- Liver problems. Your healthcare provider will do blood tests before and during your treatment with INLYTA. Your healthcare provider may delay or stop your treatment with INLYTA if you develop severe liver problems.
  Tell your healthcare provider right way if you have any of the following symptoms:

- yellowing of your skin or the whites of your eyes
- severe nausea or vomiting
- pain on the right side of your stomach area (abdomen)

- dark urine (tea colored)
- bleeding or bruising more easily than normal

- Heart problems. When INLYTA is used with the medicine avelumab, severe heart problems can happen and can lead to death. Your healthcare provider will check you for heart problems during your treatment with INLYTA. Tell your healthcare provider right away or get medical help if you have any of the following symptoms:

- swelling of your stomach-area, legs, hands feet or ankles
- shortness of breath
- nausea or vomiting
- new or worsening chest discomfort, including pain or pressure

- weight gain
- pain or discomfort in your arms, back, neck, or jaw
- breaking out in a cold sweat
- feeling lightheaded or dizzy

The most common side effects of INLYTA with avelumab include:

- diarrhea
- feeling tired
- high blood pressure
- muscle and bone pain
- nausea
- mouth sores
- rash, redness, itching, or peeling of your skin on your hands and feet
- hoarseness
- decreased appetite

- low levels of thyroid hormone
- rash
- liver problems
- cough
- shortness of breath
- stomach-area (abdomen) pain
- headache

The most common side effects of INLYTA with pembrolizumab include:

- diarrhea
- feeling tired or weak
- high blood pressure
- liver problems
- low levels of thyroid hormone
- decreased appetite
- rash, redness, itching or peeling of your skin on your hands and feet

- nausea
- mouth sores or swelling of the lining of the mouth, nose, eyes, throat, intestines, or vagina
- hoarseness
- rash
- cough
- constipation

The most common side effects of INLYTA when used alone include:

- diarrhea
- high blood pressure
- feeling tired or weak
- decreased appetite
- nausea
- hoarseness

- rash, redness, itching or peeling of your skin on your hands and feet
- decreased weight
- vomiting
- constipation

INLYTA may cause fertility problems in males and females, which may affect your ability to have a child. Talk to your healthcare provider if this is a concern for you.
These are not all of the possible side effects of INLYTA.
Call your doctor for medical advice about side effects. You may report side effects to FDA at 1-800-FDA-1088.

How should I store INLYTA?

Store INLYTA at room temperature between 68°F to 77°F (20°C to 25°C).

Keep INLYTA and all medicines out of the reach of children.

General information about the safe and effective use of INLYTA.
Medicines are sometimes prescribed for purposes other than those listed in a Patient Information leaflet. Do not use INLYTA for a condition for which it was not prescribed. Do not give INLYTA to other people, even if they have the same symptoms you have. It may harm them. You can ask your healthcare provider or pharmacist for information about INLYTA that is written for health professionals.

What are the ingredients in INLYTA?
Active ingredient: axitinib
Inactive ingredients: microcrystalline cellulose, lactose monohydrate, croscarmellose sodium, magnesium stearate, and Opadry® II red 32K15441. The Opadry II red 32K15441 film coating contains: lactose monohydrate, HPMC 2910/Hypromellose 15cP, titanium dioxide, triacetin (glycerol triacetate), and red iron oxide.

LAB-0439-8.0

For more information, go to www.inlyta.com or call 877-0744-5675
This product's labeling may have been updated. For the most recent prescribing information, please visit www.pfizer.com.

This Patient Information has been approved by the U.S. Food and Drug Administration. Revised: 07/2024

PRINCIPAL DISPLAY PANEL - 1 mg Tablet Bottle Label

Pfizer

NDC 0069-0145-01

Inlyta®
(axitinib) tablets

1 mg

180 Tablets

Rx only

PRINCIPAL DISPLAY PANEL - 5 mg Tablet Bottle Label

Pfizer

NDC 0069-0151-11

Inlyta®
(axitinib) tablets

5 mg

60 Tablets

Rx only